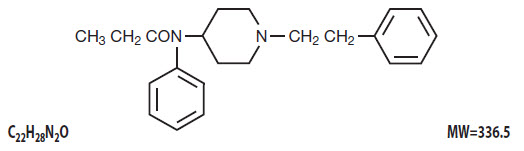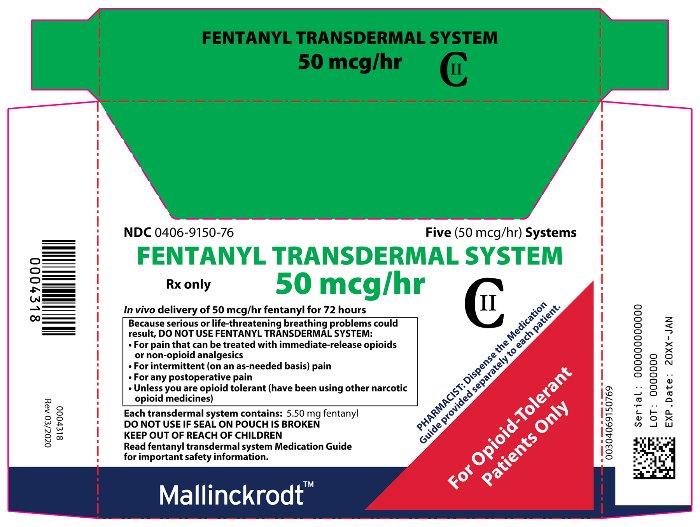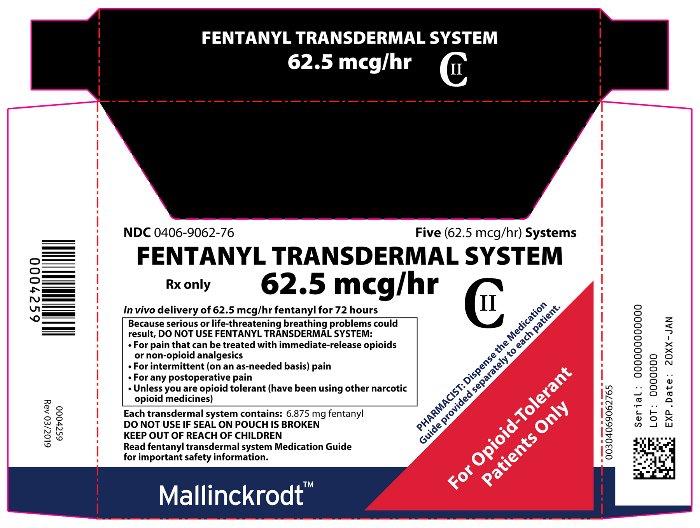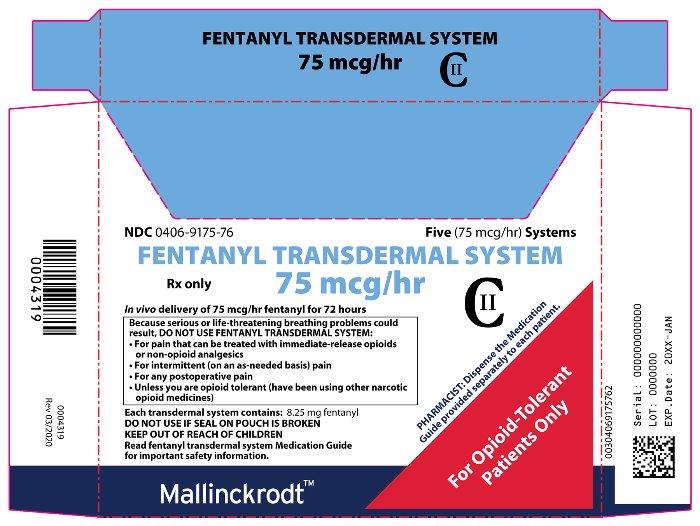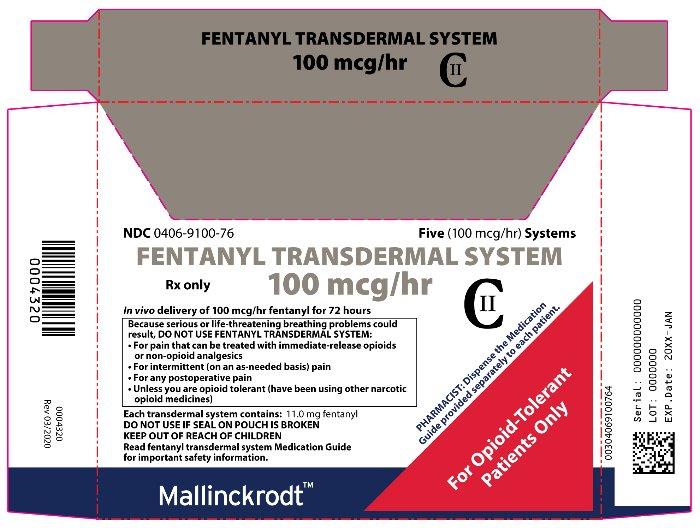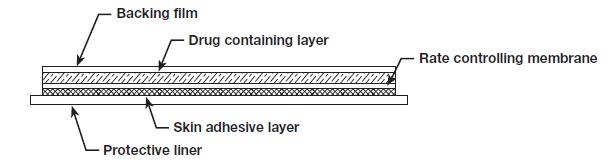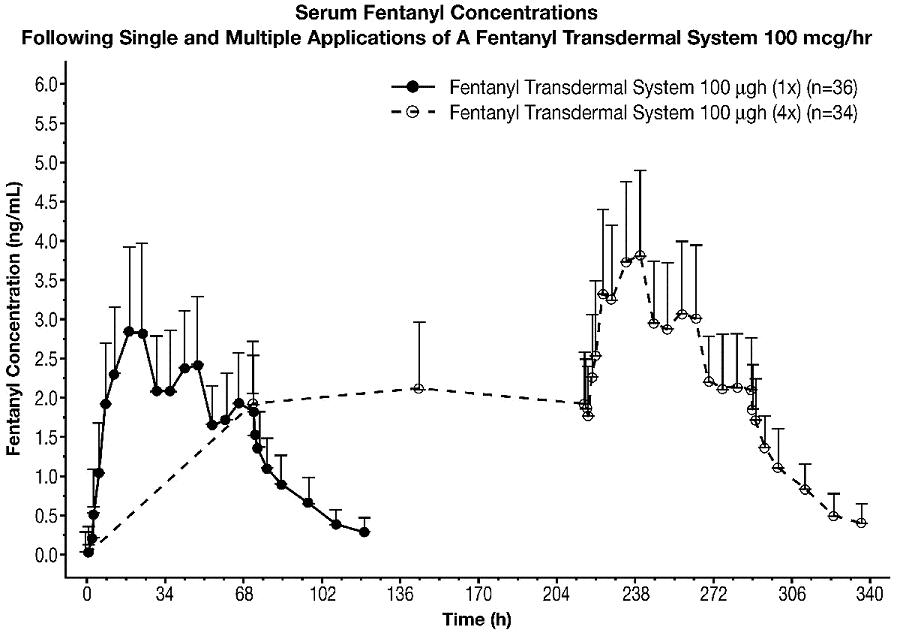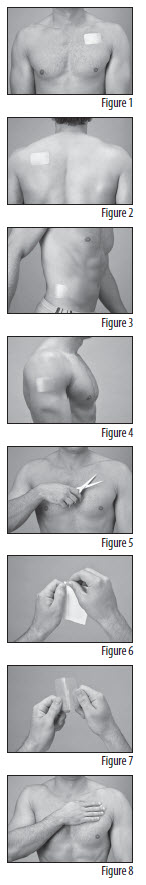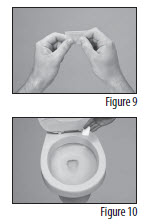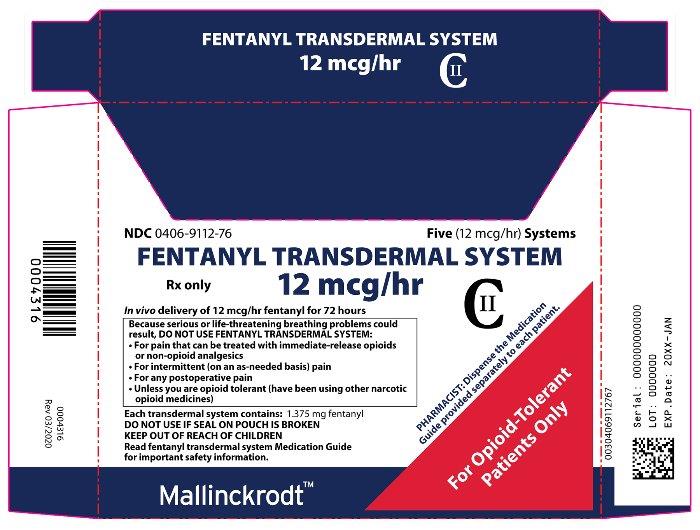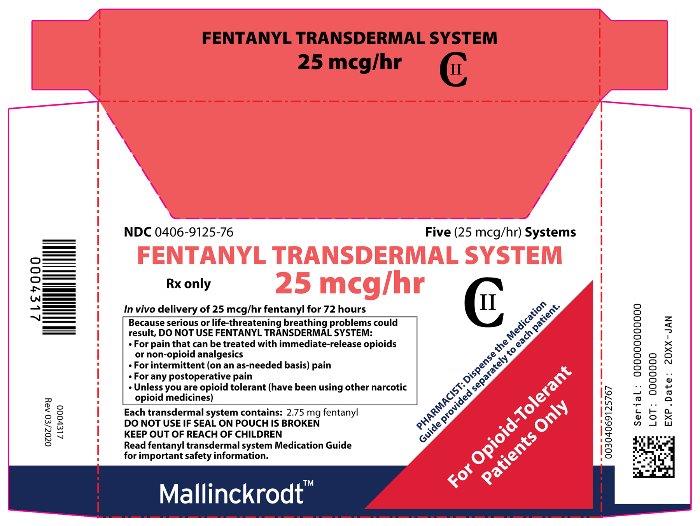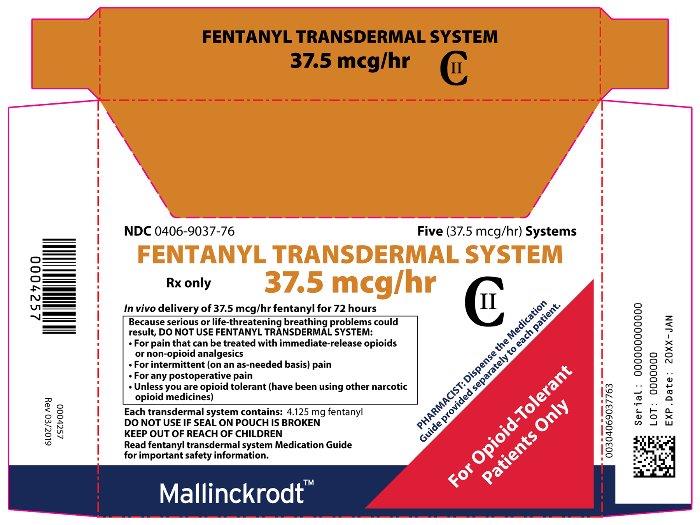 DRUG LABEL: FENTANYL TRANSDERMAL
NDC: 0406-9112 | Form: PATCH, EXTENDED RELEASE
Manufacturer: SpecGx LLC
Category: prescription | Type: HUMAN PRESCRIPTION DRUG LABEL
Date: 20251224
DEA Schedule: CII

ACTIVE INGREDIENTS: FENTANYL 12.5 ug/1 h
INACTIVE INGREDIENTS: HYDROXYPROPYL CELLULOSE (1200000 WAMW); ETHYLENE-VINYL ACETATE COPOLYMER (19% VINYLACETATE); DIPROPYLENE GLYCOL; DIMETHICONE; DIMETHICONE 350; HEPTANE

HIGHLIGHTS OF PRESCRIBING INFORMATION

These highlights do not include all the information needed to use FENTANYL TRANSDERMAL SYSTEM safely and effectively. See full prescribing information for FENTANYL TRANSDERMAL SYSTEM.
FENTANYL transdermal system, CII
Initial U.S. Approval: 1968

WARNING: SERIOUS AND LIFE-THREATENING RISKS FROM USE OF FENTANYL TRANSDERMAL SYSTEM

See full prescribing information for complete boxed warning.

- Fentanyl transdermal system exposes users to risks of addiction, abuse, and misuse, which can lead to overdose and death. Assess patient’s risk before prescribing and reassess regularly for these behaviors or conditions. (5.1)
- Serious, life-threatening, or fatal respiratory depression may occur, especially upon initiation or following a dosage increase. To reduce the risk of respiratory depression, proper dosing and titration of fentanyl transdermal system are essential. (5.2)
- Accidental exposure to fentanyl transdermal system, especially in children, can result in fatal overdose of fentanyl. (5.3)
- Concomitant use of opioids with benzodiazepines or other central nervous system (CNS) depressants, including alcohol, may result in profound sedation, respiratory depression, coma, and death. Reserve concomitant prescribing for use in patients for whom alternative treatment options are inadequate. (5.4, 7)
- Advise pregnant women using opioids for an extended period of time of the risk of Neonatal Opioid Withdrawal Syndrome, which may be life-threatening if not recognized and treated. Ensure that management by neonatology experts will be available at delivery. (5.5)
- Healthcare providers are strongly encouraged to complete a REMS compliant education program and to counsel patients and caregivers on serious risks, safe use, and the importance of reading the Medication Guide with each prescription. (5.6)
- Concomitant use with CYP3A4 inhibitors (or discontinuation of CYP3A4 inducers) can result in a fatal overdose of fentanyl. (5.7)
- Exposure of the fentanyl transdermal system application site and surrounding area to direct external heat sources has resulted in fatal overdose of fentanyl. Warn patients to avoid exposing the fentanyl transdermal system application site and surrounding area to direct external heat sources. (5.8)

RECENT MAJOR CHANGES

Boxed Warning | 12/2025
Indications and Usage (1) | 12/2025
Dosage and Administration (2.1, 2.2, 2.3, 2.9) | 12/2025
Warnings and Precautions (5.1, 5.2, 5.4, 5.19, 5.21) | 12/2025

1 INDICATIONS AND USAGE

Fentanyl transdermal system contains fentanyl, an opioid agonist, and is indicated for the management of severe and persistent pain in opioid-tolerant patients that requires an opioid analgesic and that cannot be adequately treated with alternative options, including immediate-release opioids. (1)

Patients considered opioid-tolerant are those taking, for one week or longer, at least 60 mg oral morphine per day, 25 mcg transdermal fentanyl per hour, 30 mg oral oxycodone per day, 8 mg oral hydromorphone per day, 25 mg oral oxymorphone per day, 60 mg oral hydrocodone per day, or an equianalgesic dose of another opioid. (2.1)

Limitations of Use:

• Because of the risks of addiction, abuse, misuse, overdose, and death, which can occur at any dosage or duration and persist over the course of therapy reserve opioid analgesics, including fentanyl transdermal system, for use in patients for whom alternative treatment options are ineffective, not tolerated, or would be otherwise inadequate to provide sufficient management of pain. (1, 5.1)

- Fentanyl transdermal system is not indicated as an as-needed (prn) analgesic. (1)

2 DOSAGE AND ADMINISTRATION

- Fentanyl transdermal system should be prescribed only by healthcare providers who are knowledgeable about the use of extended-release/long-acting opioids and how to mitigate the associated risks. (2.1)
- Use the lowest effective dosage for the shortest duration of time consistent with individual patient treatment goals. Reserve titration to higher doses of fentanyl transdermal system for patients in whom lower doses are insufficiently effective and in whom the expected benefits of using a higher dose opioid clearly outweigh the substantial risks. (2.1, 5)
- Initiate the dosing regimen for each patient individually, taking into account the patient’s underlying cause and severity of pain, prior analgesic treatment and response, and risk factors for addiction, abuse, and misuse. (5.1)
- Respiratory depression can occur at any time during opioid therapy, especially when initiating and following dosage increases with fentanyl transdermal system. Consider this risk when selecting an initial dose and when making dose adjustments. (2.1, 5.2)
- Discuss opioid overdose reversal agents and options for acquiring them with the patient and/or caregiver, both when initiating and renewing treatment with fentanyl transdermal system, especially if the patient has additional risk factors for overdose, or close contacts at risk for exposure and overdose. (2.2, 5.1, 5.2, 5.4)
- Initial dose selection: consult conversion instructions. (2.3)
- Periodically reassess patients receiving fentanyl transdermal system to evaluate the continued need for opioid analgesics to maintain pain control, for the signs or symptoms of adverse reactions, and for the development of addiction, abuse, or misuse. (2.4)
- Each transdermal system is intended to be worn continuously for up to 72 hours. (2.3, 2.7)
- Adhere to instructions concerning administration and disposal of fentanyl transdermal system. (2.7, 2.8)
- Mild to moderate hepatic and renal impairment: Initiate treatment with one-half the usual starting dose, titrate slowly, and regularly evaluate for signs of respiratory and central nervous system depression. (2.5, 2.6)
- Do not rapidly reduce or abruptly discontinue fentanyl transdermal system in a physically-dependent patient because rapid reduction or abrupt discontinuation of opioid analgesics has resulted in serious withdrawal symptoms, uncontrolled pain, and suicide. (2.9, 5.21)

3 DOSAGE FORMS AND STRENGTHS

Transdermal System: 12 mcg/hour, 25 mcg/hour, 37.5 mcg/hour, 50 mcg/hour, 62.5 mcg/hour, 75 mcg/hour, 100 mcg/hour. (3)

4 CONTRAINDICATIONS

- Opioid non-tolerant patients. (4)
- Acute or intermittent pain, postoperative pain, mild pain. (4)
- Significant respiratory depression. (4)
- Acute or severe bronchial asthma in an unmonitored setting or in absence of resuscitative equipment. (4)
- Known or suspected gastrointestinal obstruction, including paralytic ileus. (4)
- Known hypersensitivity to fentanyl or any of the components of the transdermal system. (4)

5 WARNINGS AND PRECAUTIONS

- Risk of Increased Fentanyl Absorption with Elevated Body Temperature: Regularly evaluate patients with fever closely for sedation and respiratory depression and reduce the dose if necessary. Warn patients to avoid strenuous exertion that may lead to increased body temperature. (5.9)
- Opioid-Induced Hyperalgesia (OIH) and Allodynia: Opioid-Induced Hyperalgesia (OIH) occurs when an opioid analgesic paradoxically causes an increase in pain, or an increase in sensitivity to pain. If OIH is suspected, carefully consider appropriately decreasing the dose of the current opioid analgesic or opioid rotation. (5.10)
- Serotonin Syndrome with Concomitant Use of Serotonergic Drugs: Potentially life-threatening condition could result from concomitant serotonergic drug administration. Discontinue fentanyl transdermal system immediately if serotonin syndrome is suspected. (5.11)
- Life-Threatening Respiratory Depression in Patients with Chronic Pulmonary Disease or in Elderly, Cachectic, or Debilitated Patients: Regularly evaluate, particularly during initiation and titration. (5.12)
- Adrenal Insufficiency: If diagnosed, treat with physiologic replacement of corticosteroids, and wean patient off of the opioid. (5.13)
- Severe Hypotension: Regularly evaluate during dose initiation and titration. Avoid the use of fentanyl transdermal system in patients with circulatory shock. (5.14)
- Risks of Use in Patients with Increased Intracranial Pressure, Brain Tumors, Head Injury or Impaired Consciousness: Monitor for sedation and respiratory depression. Avoid use of fentanyl transdermal system in patients with impaired consciousness or coma. (5.15)

6 ADVERSE REACTIONS

Most common adverse reactions (≥5%) are nausea, vomiting, somnolence, dizziness, insomnia, constipation, hyperhidrosis, fatigue, feeling cold, anorexia, headache, and diarrhea. (6)

To report SUSPECTED ADVERSE REACTIONS, contact Mallinckrodt at 1-800-778-7898 or FDA at 1-800-FDA-1088 or www.fda.gov/medwatch.

7 DRUG INTERACTIONS

Mixed Agonist/Antagonist and Partial Agonist Opioid Analgesics: Avoid use with fentanyl transdermal system because they may reduce analgesic effect of fentanyl transdermal system or precipitate withdrawal symptoms. (5.21, 7)

8 USE IN SPECIFIC POPULATIONS

- Pregnancy: May cause fetal harm. (8.1)
- Lactation: Not recommended. (8.2)
- Severe Hepatic and Renal Impairment: Use not recommended. (8.6, 8.7)

FULL PRESCRIBING INFORMATION

WARNING: SERIOUS AND LIFE-THREATENING RISKS FROM USE OF FENTANYL TRANSDERMAL SYSTEM

Addiction, Abuse, and Misuse
Because the use of fentanyl transdermal system exposes patients and other users to the risks of opioid addiction, abuse, and misuse, which can lead to overdose and death, assess each patient’s risk prior to prescribing and reassess all patients regularly for the development of these behaviors and conditions [see Warnings and Precautions (5.1)].

Life-Threatening Respiratory Depression
Serious, life-threatening, or fatal respiratory depression may occur with use of fentanyl transdermal system, especially during initiation or following a dosage increase. To reduce the risk of respiratory depression, proper dosing and titration of fentanyl transdermal system are essential [see Warnings and Precautions (5.2)].

Accidental Exposure
Accidental exposure of even one dose of fentanyl transdermal system, especially in children, can result in a fatal overdose of fentanyl [see Warnings and Precautions (5.3)]. Deaths due to an overdose of fentanyl have occurred when children and adults were accidentally exposed to fentanyl transdermal system. Strict adherence to the recommended handling and disposal instructions is of the utmost importance to prevent accidental exposure [see Warnings and Precautions (5.3)].

Risks From Concomitant Use With Benzodiazepines Or Other CNS Depressants
Concomitant use of opioids with benzodiazepines or other central nervous system (CNS) depressants, including alcohol, may result in profound sedation, respiratory depression, coma, and death. Reserve concomitant prescribing of fentanyl transdermal system and benzodiazepines or other CNS depressants for use in patients for whom alternative treatment options are inadequate [see Warnings and Precautions (5.4), Drug Interactions (7)].

Neonatal Opioid Withdrawal Syndrome (NOWS)

Advise pregnant women using opioids for an extended period of time of the risk of Neonatal Opioid Withdrawal Syndrome, which may be life-threatening if not recognized and treated. Ensure that management by neonatology experts will be available at delivery [see Warnings and Precautions (5.5)].

Opioid Analgesic Risk Evaluation and Mitigation Strategy (REMS)
Healthcare providers are strongly encouraged to complete a REMS-compliant education program and to counsel patients and caregivers on serious risks, safe use, and the importance of reading the Medication Guide with each prescription [see Warnings and Precautions (5.6)].

Cytochrome P450 3A4 Interaction
The concomitant use of fentanyl transdermal system with all cytochrome P450 3A4 inhibitors may result in an increase in fentanyl plasma concentrations, which could increase or prolong adverse drug effects and may cause potentially fatal respiratory depression. In addition, discontinuation of a concomitantly used cytochrome P450 3A4 inducer may result in an increase in fentanyl plasma concentration. Monitor patients receiving fentanyl transdermal system and any CYP 3A4 inhibitor or inducer [see Warnings and Precautions (5.7) and Clinical Pharmacology (12.3)].

Risk of Increased Fentanyl Absorption with Application of External Heat
Exposure of the fentanyl transdermal system application site and surrounding area to direct external heat sources, such as heating pads or electric blankets, heat or tanning lamps, sunbathing, hot baths, saunas, hot tubs, and heated water beds may increase fentanyl absorption and has resulted in fatal overdose of fentanyl. Warn patients to avoid exposing the application site and surrounding area to direct external heat sources [see Warnings and Precautions (5.8)].

RECENT MAJOR CHANGES

Indications and Usage (1) | 04/2023
Dosage and Administration (2.1, 2.3) | 04/2023
Warnings and Precautions (5.1, 5.2, 5.4, 5,5, 5.10) | 04/2023

1 INDICATIONS AND USAGE

Fentanyl transdermal system is indicated for the management of severe and persistent pain in opioid-tolerant patients that requires an opioid analgesic and that cannot be adequately treated with alternative options, including immediate-release opioids.

Patients considered opioid-tolerant are those who are taking, for one week or longer, at least 60 mg morphine per day, 25 mcg transdermal fentanyl per hour, 30 mg oral oxycodone per day, 8 mg oral hydromorphone per day, 25 mg oral oxymorphone per day, 60 mg oral hydrocodone per day, or an equianalgesic dose of another opioid.

Limitations of Use

- Because of the risks of addiction, abuse, misuse, overdose, and death, which can occur at any dosage or duration and persist over the course of therapy [see Warnings and Precautions (5.1)], reserve opioid analgesics, including fentanyl transdermal system, for use in patients for whom alternative treatment options are ineffective, not tolerated, or would be otherwise inadequate to provide sufficient management of pain.
- Fentanyl transdermal system is not indicated as an as-needed (prn) analgesic.

2 DOSAGE AND ADMINISTRATION

2.1 Important Dosage and Administration Instructions

- Fentanyl transdermal system should be prescribed only by healthcare professionals who are knowledgeable about the use of extended-release/long-acting opioids and how to mitigate the associated risks.
- Due to the risk of respiratory depression, fentanyl transdermal system is only indicated for use in patients who are already opioid-tolerant. Discontinue or taper all other extended-release opioids when beginning fentanyl transdermal system therapy. As fentanyl transdermal system is only for use in opioid-tolerant patients, do not begin any patient on fentanyl transdermal system as the first opioid [see Indications and Usage (1)].
- Use the lowest effective dosage for the shortest duration of time consistent with individual patient treatment goals [see Warnings and Precautions (5)]. Because the risk of overdose increases as opioid doses increase, reserve titration to higher doses of fentanyl transdermal system for patients in whom lower doses are insufficiently effective and in whom the expected benefits of using a higher dose opioid clearly outweigh the substantial risks.
- Initiate the dosing regimen for each patient individually, taking into account the patient’s underlying cause and severity of pain, prior analgesic treatment and response, and risk factors for addiction, abuse, and misuse [see Warnings and Precautions (5.1)].
- Respiratory depression can occur at any time during opioid therapy, especially when initiating and following dosage increases with fentanyl transdermal system. Consider this risk when selecting an initial dose and when making dose adjustments [see Warnings and Precautions (5)].
- Each fentanyl transdermal system is worn continuously for up to 72 hours [see Dosage and Administration (2.7)].

2.2 Patient Access to an Opioid Overdose Reversal Agent for the Emergency Treatment of Opioid Overdose

Inform patients and caregivers about opioid overdose reversal agents (e.g., naloxone, nalmefene). Discuss the importance of having access to an opioid overdose reversal agent, especially if the patient has risk factors for overdose (e.g., concomitant use of CNS depressants, a history of opioid use disorder, or prior opioid overdose) or if there are household members (including children) or other close contacts at risk for accidental ingestion or opioid overdose. The presence of risk factors for overdose should not prevent the management of pain in any patient [see Warnings and Precautions (5.1, 5.2, 5.4)].

Discuss the options for obtaining an opioid overdose reversal agent (e.g., prescription, over-the-counter, or as part of a community-based program) [see Warnings and Precautions (5.2)].

There are important differences among the opioid overdose reversal agents, such as route of administration, product strength, approved patient age range, and pharmacokinetics. Be familiar with these differences, as outlined in the approved labeling for those products, prior to recommending or prescribing such an agent.

2.3 Initial Dosage

It is safer to underestimate a patient’s 24-hour fentanyl dosage and provide rescue medication (e.g., immediate-release opioid) than to overestimate the 24-hour fentanyl dosage and manage an adverse reaction due to an overdose. While useful tables of opioid equivalents are readily available, there is inter-patient variability in the potency of opioid drugs and opioid formulations. Frequently reevaluate patients for signs and symptoms of opioid withdrawal and for signs of oversedation/toxicity after converting patients to fentanyl transdermal system.

- Do not initiate treatment with fentanyl transdermal system in patients who are not opioid tolerant [see Contraindications (4)].
- The recommended starting dose when converting from other opioids to fentanyl transdermal system is intended to minimize the potential for overdosing patients with the first dose.
- When fentanyl transdermal system therapy is initiated, discontinue all opioid analgesics other than those used on an as needed basis for breakthrough pain when appropriate.
- Each fentanyl transdermal system is worn continuously for up to 72 hours [see Dosage and Administration (2.7)].

In a fentanyl transdermal system clinical trial, patients were converted from their prior opioid to fentanyl transdermal system using Table 1 as a guide for the initial fentanyl transdermal system dose.

When converting patients from oral or parenteral opioids to fentanyl transdermal system, use Table 1 (alternatively use Table 2 for adult and pediatric patients taking opioids or doses not listed in Table 1) and consider the following:

- These are not tables of equianalgesic doses.
- The conversion doses in these tables are only for the conversion from one of the listed oral or parenteral opioid analgesics to fentanyl transdermal system.
- The tables cannot be used to convert from fentanyl transdermal system to another opioid because these conversions will result in an overestimation of the dose of the new opioid (these conversions are conservative) and may result in fatal overdosage.

Table 1 [Table 1 should not be used to convert from fentanyl transdermal system to other therapies because this conversion to fentanyl transdermal system is conservative. Use of Table 1 for conversion to other analgesic therapies can overestimate the dose of the new agent. Overdosage of the new analgesic agent is possible [see Dosage and Administration (2.9)].] . Dose Conversion from Other Opioids to Fentanyl Transdermal System
Current Analgesic | Daily Dosage (mg/day)
Oral morphine | 60-134 | 135-224 | 225-314 | 315-404
Intramuscular or Intravenous morphine | 10-22 | 23-37 | 38-52 | 53-67
Oral oxycodone | 30-67 | 67.5-112 | 112.5-157 | 157.5-202
Oral codeine | 150-447
Oral hydromorphone | 8-17 | 17.1-28 | 28.1-39 | 39.1-51
Intravenous hydromorphone | 1.5-3.4 | 3.5-5.6 | 5.7-7.9 | 8-10
Intramuscular meperidine | 75-165 | 166-278 | 279-390 | 391-503
Oral methadone | 20-44 | 45-74 | 75-104 | 105-134
Recommended Fentanyl Transdermal System Dose | 25 mcg/hour | 50 mcg/hour | 75 mcg/hour | 100 mcg/hour

Alternatively, for adult and pediatric patients taking opioids or doses not listed in Table 1, use the following methodology when converting patients from oral or parenteral opioids to fentanyl transdermal system:

1. Calculate the previous 24-hour analgesic requirement.
2. Convert this amount to the equianalgesic oral morphine dose using a reliable reference.
3. Refer to Table 2 for the range of 24-hour oral morphine doses that are recommended for conversion to each fentanyl transdermal system dose. Use this table to find the calculated 24-hour morphine dose and the corresponding recommended initial fentanyl transdermal system dose.
4. Initiate fentanyl transdermal system treatment using the recommended dose and titrate patients upwards (no more frequently than 3 days after the initial dose and every 6 days thereafter) until analgesic efficacy is attained. A 37.5 mcg/hour dose may also be used. For patients that require more than 100 mcg/hour, several transdermal systems may be used.
5. Do not use Table 2 to convert from fentanyl transdermal system to other therapies because this conversion to fentanyl transdermal system is conservative and will overestimate the dose of the new agent.

Table 2 [Table 2 should not be used to convert from fentanyl transdermal system to other therapies because this conversion to fentanyl transdermal system is conservative. Use of Table 2 for conversion to other analgesic therapies can overestimate the dose of the new agent. Overdosage of the new analgesic agent is possible [see Dosage and Administration (2.9)].] . Recommended Initial Fentanyl Transdermal System Dose Based Upon Daily Oral Morphine Dose
Oral 24-hour Morphine (mg/day) | Fentanyl Transdermal System Dose (mcg/hour)
60-134 | 25
135-224 | 50
225-314 | 75
315-404 | 100
405-494 | 125
495-584 | 150
585-674 | 175
675-764 | 200
765-854 | 225
855-944 | 250
945-1034 | 275
1035-1124 | 300

NOTE: In clinical trials, these ranges of daily oral morphine doses were used as a basis for conversion to fentanyl transdermal system.

Additional intermediate strengths 37.5 mcg/hr and 62.5 mcg/hr fentanyl transdermal systems are available and may be considered during conversion from prior opioids or dose titration. For example, the 37.5 mcg/hr system could be used before converting or titrating to a 50 mcg/hr system. Similarly a 62.5 mcg/hr system is available for use as an intermediate strength between the 50 mcg/hr and the 75 mcg/hr system.

The additional intermediate strengths, 37.5 mcg/hr and 62.5 mcg/hr, were not used in the clinical studies.

For delivery rates in excess of 100 mcg/hr, multiple systems may be used.

2.4 Titration and Maintenance of Therapy

Individually titrate fentanyl transdermal system to a dose that provides adequate analgesia and minimizes adverse reactions. Continually reevaluate patients receiving fentanyl transdermal system to assess the maintenance of pain control, signs and symptoms of opioid withdrawal, and other adverse reactions, as well as to reassess for the development of addiction, abuse, or misuse [see Warnings and Precautions (5.1, 5.21)]. Frequent communication is important among the prescriber, other members of the healthcare team, the patient, and the caregiver/family during periods of changing analgesic requirements, including initial titration. During use of opioid therapy for an extended period of time, periodically reassess the continued need for opioid analgesics.

Patients who experience breakthrough pain may require a dosage adjustment of fentanyl transdermal system, or may need rescue medication with an appropriate dose of an immediate-release analgesic. If the level of pain increases after dosage stabilization, attempt to identify the source of increased pain before increasing the fentanyl transdermal system dosage.

The dosing interval for fentanyl transdermal system is 72 hours. Do not increase the fentanyl transdermal system dose for the first time until at least 3 days after the initial application. Titrate the dose based on the daily dose of supplemental opioid analgesics required by the patient on the second or third day of the initial application.

It may take up to 6 days for fentanyl levels to reach equilibrium on a new dose [see Clinical Pharmacology (12.3)]. Therefore, evaluate patients for further titration after no less than two 3-day applications before any further increase in dosage is made.

Base dosage increments on the daily dosage of supplementary opioids, using the ratio of 45 mg/24 hours of oral morphine to a 12 mcg/hour increase in fentanyl transdermal system dose.

If after increasing the dosage, unacceptable opioid-related adverse reactions are observed (including an increase in pain after dosage increase), consider reducing the dosage [see Warnings and Precautions (5)]. Adjust the dose to obtain an appropriate balance between management of pain and opioid-related adverse reactions.

A small proportion of adult patients may not achieve adequate analgesia using a 72-hour dosing interval and may require systems to be applied at 48 hours rather than at 72 hours, only if adequate pain control cannot be achieved using a 72-hour regimen. An increase in the fentanyl transdermal system dose should be evaluated before changing dosing intervals in order to maintain patients on a 72-hour regimen.

Dosing intervals less than every 72 hours were not studied in children and adolescents and are not recommended.

2.5 Dosage Modifications in Patients with Hepatic Impairment

Avoid the use of fentanyl transdermal system in patients with severe hepatic impairment. In patients with mild to moderate hepatic impairment, start with one-half of the usual dosage of fentanyl transdermal system. Closely monitor for signs of respiratory and central nervous system depression, including at each dosage increase [see Warnings and Precautions (5.17), Use in Specific Populations (8.6) and Clinical Pharmacology (12.3)].

2.6 Dosage Modifications in Patients with Renal Impairment

Avoid the use of fentanyl transdermal system in patients with severe renal impairment. In patients with mild to moderate renal impairment, start with one-half of the usual dosage of fentanyl transdermal system. Closely monitor for signs of respiratory and central nervous system depression, including at each dosage increase [see Warnings and Precautions (5.18), Use in Specific Populations (8.7) and Clinical Pharmacology (12.3)].

2.7 Administration of Fentanyl Transdermal System

FENTANYL TRANSDERMAL SYSTEMS ARE FOR TRANSDERMAL USE ONLY.

Proper handling of fentanyl transdermal system is necessary in order to prevent serious adverse outcomes, including death, associated with accidental secondary exposure to fentanyl transdermal system [see Warnings and Precautions (5.3)].

Application and Handling Instructions

- Patients should apply fentanyl transdermal system to intact, non-irritated, and non-irradiated skin on a flat surface such as the chest, back, flank, or upper arm. In young children and persons with cognitive impairment, adhesion should be monitored and the upper back is the preferred location to minimize the potential of inappropriate patch removal. Hair at the application site may be clipped (not shaved) prior to system application. If the site of fentanyl transdermal system application must be cleansed prior to application of the patch, do so with clear water. Do not use soaps, oils, lotions, alcohol, or any other agents that might irritate the skin or alter its characteristics. Allow the skin to dry completely prior to patch application.
- Patients should apply fentanyl transdermal system immediately upon removal from the sealed package. The patch must not be altered (e.g., cut) in any way prior to application. Fentanyl transdermal system should not be used if the pouch seal is broken or if the patch is cut or damaged.
- The transdermal system is pressed firmly in place with the palm of the hand for 30 seconds, making sure the contact is complete, especially around the edges.
- Each fentanyl transdermal system may be worn continuously for 72 hours. The next patch is applied to a different skin site after removal of the previous transdermal system.
- If problems with adhesion of the fentanyl transdermal system occur, the edges of the patch may be taped with first aid tape. If problems with adhesion persist, the patch may be overlayed with a transparent adhesive film dressing.
- If the patch falls off before 72 hours, dispose of it by folding in half and flushing down the toilet. A new patch may be applied to a different skin site.
- Patients (or caregivers who apply fentanyl transdermal system) should wash their hands immediately with soap and water after applying fentanyl transdermal system.
- Contact with unwashed or unclothed application sites can result in secondary exposure to fentanyl transdermal system and should be avoided. Examples of accidental exposure include transfer of a fentanyl transdermal system from an adult’s body to a child while hugging, sharing the same bed as the patient, accidental sitting on a patch and possible accidental exposure of a caregiver’s skin to the medication in the patch while applying or removing the patch.
- Instruct patients, family members, and caregivers to keep patches in a secure location out of the reach of children and of others for whom fentanyl transdermal system was not prescribed.

Avoidance of Heat

Instruct patients to avoid exposing the fentanyl transdermal system application site and surrounding area to direct external heat sources, such as heating pads or electric blankets, heat or tanning lamps, sunbathing, hot baths, saunas, hot tubs, and heated waterbeds, while wearing the system [see Warnings and Precautions (5.8)].

2.8 Disposal Instructions

Failure to properly dispose of fentanyl transdermal system has resulted in accidental exposures and deaths, including deaths of children [see Warnings and Precautions (5.3)].

Instruct patients to dispose of used patches immediately upon removal by folding the adhesive side of the patch to itself, then flushing down the toilet.

Instruct patients to remove unused patches from their pouches, remove the protective liners, fold the patches so that the adhesive side of the patch adheres to itself, and to immediately flush the patches down the toilet.

Instruct patients to dispose of any patches remaining from a prescription as soon as they are no longer needed.

2.9 Safe Reduction or Discontinuation of Fentanyl Transdermal System

Do not rapidly reduce or abruptly discontinue fentanyl transdermal system in patients who may be physically dependent on opioids. Rapid reduction or abrupt discontinuation of opioid analgesics in patients who are physically dependent on opioids has resulted in serious withdrawal symptoms, uncontrolled pain, and suicide. Rapid reduction or abrupt discontinuation has also been associated with attempts to find other sources of opioid analgesics, which may be confused with drug-seeking for abuse. Patients may also attempt to treat their pain or withdrawal symptoms with illicit opioids, such as heroin, and other substances.

When a decision has been made to decrease the dose or discontinue therapy in an opioid-dependent patient taking fentanyl transdermal system, there are a variety of factors that should be considered, including the total daily dose of opioid (including fentanyl transdermal system) the patient has been taking, the duration of treatment, the type of pain being treated, and the physical and psychological attributes of the patient. It is important to ensure ongoing care of the patient and to agree on an appropriate tapering schedule and follow-up plan so that patient and provider goals and expectations are clear and realistic. When opioid analgesics are being discontinued due to a suspected substance use disorder, evaluate and treat the patient, or refer for evaluation and treatment of the substance use disorder. Treatment should include evidence-based approaches, such as medication assisted treatment of opioid use disorder. Complex patients with comorbid pain and substance use disorders may benefit from referral to a specialist.

There are no standard opioid tapering schedules that are suitable for all patients. Good clinical practice dictates a patient-specific plan to taper the dose of the opioid gradually. For patients on fentanyl transdermal system who are physically opioid-dependent, initiate the taper by a small enough increment (e.g., no greater than 25% of the total daily dose) to avoid withdrawal symptoms, and proceed with dose-lowering at an interval of every 2 to 4 weeks. Patients who have been taking opioids for briefer periods of time may tolerate a more rapid taper.

It may be necessary to provide the patient with a lower dosage strength to accomplish a successful taper. Reassess the patient frequently to manage pain and withdrawal symptoms, should they emerge. Common withdrawal symptoms include restlessness, lacrimation, rhinorrhea, yawning, perspiration, chills, myalgia, and mydriasis. Other signs and symptoms also may develop, including irritability, anxiety, backache, joint pain, weakness, abdominal cramps, insomnia, nausea, anorexia, vomiting, diarrhea, or increased blood pressure, respiratory rate, or heart rate. If withdrawal symptoms arise, it may be necessary to pause the taper for a period of time or raise the dose of the opioid analgesic to the previous dose, and then proceed with a slower taper. In addition, evaluate patients for any changes in mood, emergence of suicidal thoughts, or use of other substances.

When managing patients taking opioid analgesics, particularly those who have been treated for an extended period of time, and/or with high doses for chronic pain, ensure that a multimodal approach to pain management, including mental health support (if needed), is in place prior to initiating an opioid analgesic taper. A multimodal approach to pain management may optimize the treatment of chronic pain, as well as assist with the successful tapering of the opioid analgesic [see Warnings and Precautions (5.21), Drug Abuse and Dependence (9.3)].

3 DOSAGE FORMS AND STRENGTHS

Fentanyl transdermal systems are a rectangular, opaque patch with rounded corners:

- Fentanyl Transdermal System 12 mcg/hour* (system size 3.9 cm^2) is green in color.
- Fentanyl Transdermal System 25 mcg/hour (system size 7.8 cm^2) is green in color.
- Fentanyl Transdermal System 37.5 mcg/hour (system size 11.7 cm^2) is green in color.
- Fentanyl Transdermal System 50 mcg/hour (system size 15.6 cm^2) is green in color.
- Fentanyl Transdermal System 62.5 mcg/hour (system size 19.6 cm^2) is green in color.
- Fentanyl Transdermal System 75 mcg/hour (system size 23.4 cm^2) is green in color.
- Fentanyl Transdermal System 100 mcg/hour (system size 31.3 cm^2) is green in color.

* This lowest strength is designated as 12 mcg/hour (however, the actual strength is
12.5 mcg/hour) to distinguish it from a possible 125 mcg/hr dosage that could be prescribed by using multiple transdermal systems.

The 12 mcg/hour system has a green border and the 25, 37.5, 50, 62.5, 75 and 100 mcg/hour systems have green stripes that increase in number with each sequential increasing dosage strength.

4 CONTRAINDICATIONS

Fentanyl transdermal system is contraindicated in:

- patients who are not opioid-tolerant.
- the management of acute or intermittent pain, or in patients who require opioid analgesia for a short period of time.
- the management of post-operative pain, including use after out-patient or day surgeries, (e.g., tonsillectomies).
- the management of mild pain.
- patients with significant respiratory depression [see Warnings and Precautions (5.12)].
- in patients with acute or severe bronchial asthma in an unmonitored setting or in the absence of resuscitative equipment [see Warnings and Precautions (5.12)].
- in patients with known or suspected gastrointestinal obstruction, including paralytic ileus [see Warnings and Precautions (5.19)].
- in patients with hypersensitivity to fentanyl (e.g., anaphylaxis) or any components of the transdermal system [see Adverse Reactions (6.2)].

5 WARNINGS AND PRECAUTIONS

5.1 Addiction, Abuse, and Misuse

Fentanyl transdermal system contains fentanyl, an opioid agonist and a Schedule II controlled substance. As an opioid, fentanyl transdermal system exposes users to the risks of addiction, abuse, and misuse.

Although the risk of addiction in any individual is unknown, it can occur in patients appropriately prescribed fentanyl transdermal system. Addiction can occur at recommended doses and if the drug is misused or abused. The risk of opioid-related overdose or overdose-related death is increased with higher opioid doses, and this risk persists over the course of therapy. In postmarketing studies, addiction, abuse, misuse, and fatal and non-fatal opioid overdose were observed in patients with long-term opioid use [see Adverse Reactions (6.2)].

Assess each patient’s risk for opioid addiction, abuse, or misuse prior to prescribing fentanyl transdermal system, and reassess all patients receiving fentanyl transdermal system for the development of these behaviors and conditions. Risks are increased in patients with a personal or family history of substance abuse (including drug or alcohol abuse or addiction) or mental illness (e.g., major depression). The potential for these risks should not, however, prevent the proper management of pain in any given patient. Patients at increased risk may be prescribed opioids such as fentanyl transdermal system, but use in such patients necessitates intensive counseling about the risks and proper use of fentanyl transdermal system along with frequent reevaluation for signs of addiction, abuse, and misuse. Consider recommending or prescribing an opioid overdose reversal agent [see Dosage and Administration (2.2), Warnings and Precautions (5.2)].

Abuse or misuse of fentanyl transdermal system by placing it in the mouth, chewing it, swallowing it, or using it in ways other than indicated may cause choking, overdose, and death [see Overdosage (10)].

Opioids are sought for nonmedical use and are subject to diversion from legitimate prescribed use. Consider these risks when prescribing or dispensing fentanyl transdermal system. Strategies to reduce these risks include prescribing the drug in the smallest appropriate quantity and advising the patient on careful storage of the drug during the course of treatment and proper disposal of unused drug. Contact local state professional licensing board or state-controlled substances authority for information on how to prevent and detect abuse or diversion of this product.

5.2 Life-Threatening Respiratory Depression

Serious, life-threatening, or fatal respiratory depression has been reported with the use of opioids, even when used as recommended. Respiratory depression, if not immediately recognized and treated, may lead to respiratory arrest and death. Management of respiratory depression may include close observation, supportive measures, and use of opioid overdose reversal agents, depending on the patient’s clinical status [see Overdosage (10)]. Carbon dioxide (CO2) retention from opioid-induced respiratory depression can exacerbate the sedating effects of opioids.

Fentanyl transdermal system is indicated only in opioid tolerant patients because of the risk for respiratory depression and death. While serious, life-threatening, or fatal respiratory depression can occur at any time during the use of fentanyl transdermal system, the risk is greatest during the initiation of therapy or following a dosage increase.

To reduce the risk of respiratory depression, proper dosing and titration of fentanyl transdermal system are essential [see Dosage and Administration (2)]. Overestimating the fentanyl transdermal system dosage when converting patients from another opioid product can result in fatal overdose with the first dose.

Accidental exposure to fentanyl transdermal system, especially in children, can result in respiratory depression and death due to an overdose of fentanyl.

Educate patients and caregivers on how to recognize respiratory depression and emphasize the importance of calling 911 or getting emergency medical help right away in the event of a known or suspected overdose [see Patient Counseling Information (17)].

Opioids can cause sleep-related breathing disorders including central sleep apnea (CSA) and sleep-related hypoxemia. Opioid use increases the risk of CSA in a dose-dependent fashion. In patients who present with CSA, consider decreasing the opioid dosage using best practices for opioid taper [see Dosage and Administration (2.9)].

Patient Access to an Opioid Overdose Reversal Agent for the Emergency Treatment of Opioid Overdose

Inform patients and caregivers about opioid overdose reversal agents (e.g., naloxone, nalmefene). Discuss the importance of having access to an opioid overdose reversal agent, especially if the patient has risk factors for overdose (e.g., concomitant use of CNS depressants, a history of opioid use disorder, or prior opioid overdose) or if there are household members (including children) or other close contacts at risk for accidental ingestion or opioid overdose. The presence of risk factors for overdose should not prevent the management of pain in any patient [see Warnings and Precautions (5.1, 5.4)].

Discuss the options for obtaining an opioid overdose reversal agent (e.g., prescription, over-the-counter, or as part of a community-based program).

There are important differences among the opioid overdose reversal agents, such as route of administration, product strength, approved patient age range, and pharmacokinetics. Be familiar with these differences, as outlined in the approved labeling for those products, prior to recommending or prescribing such an agent.

Educate patients and caregivers on how to recognize respiratory depression, and how to use an opioid overdose reversal agent for the emergency treatment of opioid overdose. Emphasize the importance of calling 911 or getting emergency medical help, even if an opioid overdose reversal agent is administered [see Dosage and Administration (2.2), Warnings and Precautions (5.1, 5.4), Overdosage (10)].

5.3 Accidental Exposure

A considerable amount of active fentanyl remains in fentanyl transdermal system even after use as directed. Death and other serious medical problems have occurred when children and adults were accidentally exposed to fentanyl transdermal system. Accidental or deliberate application or ingestion by a child or adolescent will cause respiratory depression, and has resulted in deaths. Placing fentanyl transdermal system in the mouth, chewing it, swallowing it, or using it in ways other than indicated may cause choking or overdose that could result in death. Improper disposal of fentanyl transdermal system in the trash has resulted in accidental exposures and deaths.

Advise patients about strict adherence to the recommended handling and disposal instructions in order to prevent accidental exposure to fentanyl transdermal system [see Dosage and Administration (2.7), (2.8)]. Exposure to fentanyl transdermal systems discarded in the trash by children have been reported and have resulted in deaths.

5.4 Risks from Concomitant Use with Benzodiazepines or Other CNS Depressants

Profound sedation, respiratory depression, coma, and death may result from the concomitant use of fentanyl transdermal system with benzodiazepines and/or other CNS depressants, including alcohol [e.g., non-benzodiazepine sedatives/hypnotics, anxiolytics, tranquilizers, muscle relaxants, general anesthetics, antipsychotics, gabapentinoids (gabapentin or pregabalin), and other opioids]. Because of these risks, reserve concomitant prescribing of these drugs for use in patients for whom alternative treatment options are inadequate.

Observational studies have demonstrated that concomitant use of opioid analgesics and benzodiazepines increases the risk of drug-related mortality compared to use of opioid analgesics alone. Because of similar pharmacological properties, it is reasonable to expect similar risk with the concomitant use of other CNS depressant drugs with opioid analgesics [see Drug Interactions (7)].

If the decision is made to prescribe a benzodiazepine or other CNS depressant concomitantly with an opioid analgesic, prescribe the lowest effective dosages and minimum durations of concomitant use. In patients already receiving an opioid analgesic, prescribe a lower initial dose of the benzodiazepine or other CNS depressant than indicated in the absence of an opioid, and titrate based on clinical response. If an opioid analgesic is initiated in a patient already taking a benzodiazepine or other CNS depressant, prescribe a lower initial dose of the opioid analgesic, and titrate based on clinical response. Inform patients and caregivers of this potential interaction, educate them on the signs and symptoms of respiratory depression (including sedation).

If concomitant use is warranted, consider recommending or prescribing an opioid overdose reversal agent [see Dosage and Administration (2.2), Warnings and Precautions (5.2), Overdosage (10)].

Advise both patients and caregivers about the risks of respiratory depression and sedation when fentanyl transdermal system is used with benzodiazepines or other CNS depressants (including alcohol and illicit drugs). Advise patients not to drive or operate heavy machinery until the effects of concomitant use of the benzodiazepine or other CNS depressant have been determined. Screen patients for risk of substance use disorders, including opioid abuse and misuse, and warn them of the risk for overdose and death associated with the use of additional CNS depressants including alcohol and illicit drugs [see Drug Interactions (7), Patient Counseling Information (17)].

5.5 Neonatal Opioid Withdrawal Syndrome

Use of fentanyl transdermal system for an extended period of time during pregnancy can result in withdrawal in the neonate. Neonatal opioid withdrawal syndrome, unlike opioid withdrawal syndrome in adults, may be life-threatening if not recognized and treated, and requires management according to protocols developed by neonatology experts. Observe newborns for signs of neonatal opioid withdrawal syndrome and manage accordingly. Advise pregnant women using opioids for an extended period of time of the risk of neonatal opioid withdrawal syndrome and ensure that appropriate treatment will be available [see Use in Specific Populations (8.1), Patient Counseling Information (17)].

5.6 Opioid Analgesic Risk Evaluation and Mitigation Strategy (REMS)

To ensure that the benefits of opioid analgesics outweigh the risks of addiction, abuse, and misuse, the Food and Drug Administration (FDA) has required a Risk Evaluation and Mitigation Strategy (REMS) for these products. Under the requirements of the REMS, drug companies with approved opioid analgesic products must make REMS-compliant education programs available to healthcare providers. Healthcare providers are strongly encouraged to do all of the following:

- Complete a REMS-compliant education program offered by an accredited provider of continuing education (CE) or another education program that includes all the elements of the FDA Education Blueprint for Health Care Providers Involved in the Management or Support of Patients with Pain.
- Discuss the safe use, serious risks, and proper storage and disposal of opioid analgesics with patients and/or their caregivers every time these medicines are prescribed. The Patient Counseling Guide (PCG) can be obtained at this link:www.fda.gov/OpioidAnalgesicREMSPCG.
- Emphasize to patients and their caregivers the importance of reading the Medication Guide that they will receive from their pharmacist every time an opioid analgesic is dispensed to them.
- Consider using other tools to improve patient, household, and community safety, such as patient-prescriber agreements that reinforce patient-prescriber responsibilities.

To obtain further information on the opioid analgesic REMS and for a list of accredited REMS CME/CE, call 1-800-503-0784, or log on to www.opioidanalgesicrems.com. The FDA Blueprint can be found at www.fda.gov/OpioidAnalgesicREMSBlueprint.

5.7 Risks of Concomitant Use or Discontinuation of Cytochrome P450 3A4 Inhibitors and Inducers

Concomitant use of fentanyl transdermal system with a CYP3A4 inhibitor, such as macrolide antibiotics (e.g., erythromycin), azole-antifungal agents (e.g., ketoconazole), and protease inhibitors (e.g., ritonavir), may increase plasma concentrations of fentanyl and prolong opioid adverse reactions, which may cause potentially fatal respiratory depression [see Warnings and Precautions (5.2)], particularly when an inhibitor is added after a stable dose of fentanyl transdermal system is achieved. Similarly, discontinuation of a CYP3A4 inducer, such as rifampin, carbamazepine, and phenytoin, in fentanyl transdermal system-treated patients may increase fentanyl plasma concentrations and prolong opioid adverse reactions. When using fentanyl transdermal system with CYP3A4 inhibitors or discontinuing CYP3A4 inducers in fentanyl transdermal system-treated patients, evaluate patients at frequent intervals and consider dosage reduction of fentanyl transdermal system until stable drug effects are achieved [see Dosage and Administration (2.4), Drug Interactions (7)].

Concomitant use of fentanyl transdermal system with CYP3A4 inducers or discontinuation of a CYP3A4 inhibitor could decrease fentanyl transdermal system plasma concentrations, decrease opioid efficacy or, possibly, lead to a withdrawal syndrome in a patient who had developed physical dependence to fentanyl. When using fentanyl transdermal system with CYP3A4 inducers or discontinuing CYP3A4 inhibitors, monitor patients closely at frequent intervals and consider increasing the opioid dosage if needed to maintain adequate analgesia or if symptoms of opioid withdrawal occur [see Drug Interactions (7)].

5.8 Risk of Increased Fentanyl Absorption with Application of External Heat

Exposure to heat may increase fentanyl absorption and there have been reports of overdose and death as a result of exposure to heat. A clinical pharmacology study conducted in healthy adult subjects has shown that the application of heat over the fentanyl transdermal system increased fentanyl exposure [see Clinical Pharmacology (12.3)].

Warn patients to avoid exposing the fentanyl transdermal system application site and surrounding area to direct external heat sources [see Dosage and Administration (2.7)].

5.9 Risk of Increased Fentanyl Absorption with Elevated Body Temperature

Based on a pharmacokinetic model, serum fentanyl concentrations could theoretically increase by approximately one-third for patients with a body temperature of 40°C (104°F) due to temperature-dependent increases in fentanyl released from the system and increased skin permeability. Monitor patients wearing fentanyl transdermal systems who develop fever closely for sedation and respiratory depression and reduce the fentanyl transdermal system dose, if necessary. Warn patients to avoid strenuous exertion that leads to increased core body temperature while wearing fentanyl transdermal system to avoid the risk of potential overdose and death.

5.10 Opioid-Induced Hyperalgesia and Allodynia

Opioid-Induced Hyperalgesia (OIH) occurs when an opioid analgesic paradoxically causes an increase in pain, or an increase in sensitivity to pain. This condition differs from tolerance, which is the need for increasing doses of opioids to maintain a defined effect [see Dependence (9.3)].

Symptoms of OIH include (but may not be limited to) increased levels of pain upon opioid dosage increase, decreased levels of pain upon opioid dosage decrease, or pain from ordinarily non-painful stimuli (allodynia). These symptoms may suggest OIH only if there is no evidence of underlying disease progression, opioid tolerance, opioid withdrawal, or addictive behavior.

Cases of OIH have been reported, both with short-term and longer-term use of opioid analgesics. Though the mechanism of OIH is not fully understood, multiple biochemical pathways have been implicated. Medical literature suggests a strong biologic plausibility between opioid analgesics and OIH and allodynia. If a patient is suspected to be experiencing OIH, carefully consider appropriately decreasing the dose of the current opioid analgesic, or opioid rotation (safely switching the patient to a different opioid moiety) [see Dosage and Administration (2.9); Warnings and Precautions (5.21)].

5.11 Serotonin Syndrome with Concomitant Use of Serotonergic Drugs

Cases of serotonin syndrome, a potentially life-threatening condition, have been reported during concomitant use of fentanyl transdermal system with serotonergic drugs. Serotonergic drugs include selective serotonin reuptake inhibitors (SSRIs), serotonin and norepinephrine reuptake inhibitors (SNRIs), tricyclic antidepressants (TCAs), triptans, 5-HT3 receptor antagonists, drugs that affect the serotonergic neurotransmitter system (e.g., mirtazapine, trazodone, tramadol), certain muscle relaxants (i.e., cyclobenzaprine, metaxalone), and drugs that impair metabolism of serotonin (including MAO inhibitors, both those intended to treat psychiatric disorders and also others, such as linezolid and intravenous methylene blue) [see Drug Interactions (7)]. This may occur within the recommended dosage range. Serotonin syndrome symptoms may include mental status changes (e.g., agitation, hallucinations, coma), autonomic instability (e.g., tachycardia, labile blood pressure, hyperthermia), neuromuscular aberrations (e.g., hyperreflexia, incoordination, rigidity), and/or gastrointestinal symptoms (e.g., nausea, vomiting, diarrhea). The onset of symptoms generally occurs within several hours to a few days of concomitant use, but may occur later than that. Discontinue fentanyl transdermal system immediately if serotonin syndrome is suspected.

5.12 Life-Threatening Respiratory Depression in Patients with Chronic Pulmonary Disease or in Elderly, Cachectic, or Debilitated Patients

The use of fentanyl transdermal system in patients with acute or severe bronchial asthma in an unmonitored setting or in the absence of resuscitative equipment is contraindicated.

Patients with Chronic Pulmonary Disease: Fentanyl transdermal system-treated patients with significant chronic obstructive pulmonary disease or cor pulmonale, and those with a substantially decreased respiratory reserve, hypoxia, hypercapnia, or pre-existing respiratory depression are at increased risk of decreased respiratory drive including apnea, even at recommended dosages of fentanyl transdermal system [see Warnings and Precautions (5.2)].

Elderly, Cachectic, or Debilitated Patients: Life-threatening respiratory depression is more likely to occur in elderly, cachectic, or debilitated patients because they may have altered pharmacokinetics or altered clearance compared to younger, healthier patients [see Warnings and Precautions (5.2)].

Regularly evaluate patients, particularly when initiating and titrating fentanyl transdermal system and when fentanyl transdermal system is given concomitantly with other drugs that depress respiration [see Warnings and Precautions (5.2)]. Alternatively, consider the use of non-opioid analgesics in these patients.

5.13 Adrenal Insufficiency

Cases of adrenal insufficiency have been reported with opioid use, more often following greater than one month of use. Presentation of adrenal insufficiency may include non-specific symptoms and signs including nausea, vomiting, anorexia, fatigue, weakness, dizziness, and low blood pressure. If adrenal insufficiency is suspected, confirm the diagnosis with diagnostic testing as soon as possible. If adrenal insufficiency is diagnosed, treat with physiologic replacement doses of corticosteroids. Wean the patient off of the opioid to allow adrenal function to recover and continue corticosteroid treatment until adrenal function recovers. Other opioids may be tried as some cases reported use of a different opioid without recurrence of adrenal insufficiency. The information available does not identify any particular opioids as being more likely to be associated with adrenal insufficiency.

5.14 Severe Hypotension

Fentanyl transdermal system may cause severe hypotension including orthostatic hypotension and syncope in ambulatory patients. There is an increased risk in patients whose ability to maintain blood pressure has already been compromised by a reduced blood volume or concurrent administration of certain CNS depressant drugs (e.g., phenothiazines or general anesthetics) [see Drug Interactions (7)]. Regularly evaluate these patients for signs of hypotension after initiating or titrating the dosage of fentanyl transdermal system. In patients with circulatory shock, fentanyl transdermal system may cause vasodilation that can further reduce cardiac output and blood pressure. Avoid the use of fentanyl transdermal system in patients with circulatory shock.

5.15 Risks of Use in Patients with Increased Intracranial Pressure, Brain Tumors, Head Injury, or Impaired Consciousness

In patients who may be susceptible to the intracranial effects of CO2 retention (e.g., those with evidence of increased intracranial pressure or brain tumors), fentanyl transdermal system may reduce respiratory drive, and the resultant CO2 retention can further increase intracranial pressure. Monitor such patients for signs of sedation and respiratory depression, particularly when initiating therapy with fentanyl transdermal system.

Opioids may also obscure the clinical course in a patient with a head injury. Avoid the use of fentanyl transdermal system in patients with impaired consciousness or coma.

5.16 Cardiac Disease

Fentanyl transdermal system may produce bradycardia. Regularly evaluate patients with bradyarrhythmias closely for changes in heart rate, particularly when initiating therapy with fentanyl transdermal system.

5.17 Hepatic Impairment

A clinical pharmacology study with fentanyl transdermal system in patients with cirrhosis has shown that systemic fentanyl exposure increased in these patients. Because of the long half-life of fentanyl when administered as fentanyl transdermal system and hepatic metabolism of fentanyl, avoid use of fentanyl transdermal system in patients with severe hepatic impairment. Insufficient information exists to make precise dosing recommendations regarding the use of fentanyl transdermal system in patients with impaired hepatic function. Therefore, to avoid starting patients with mild to moderate hepatic impairment on too high of a dose, start with one half of the usual dosage of fentanyl transdermal system. Regularly evaluate for signs of sedation and respiratory depression, including at each dosage increase [see Dosage and Administration (2.5), Use in Specific Populations (8.6) and Clinical Pharmacology (12.3)].

5.18 Renal Impairment

A clinical pharmacology study with intravenous fentanyl in patients undergoing kidney transplantation has shown that patients with high blood urea nitrogen level had low fentanyl clearance. Because of the long half-life of fentanyl when administered as fentanyl transdermal system, avoid the use of fentanyl transdermal system in patients with severe renal impairment. Insufficient information exists to make precise dosing recommendations regarding the use of fentanyl transdermal system in patients with impaired renal function. Therefore, to avoid starting patients with mild to moderate renal impairment on too high of a dose, start with one-half of the usual dosage of fentanyl transdermal system. Regularly evaluate for signs of sedation and respiratory depression, including at each dosage increase [see Dosage and Administration (2.6), Use in Specific Populations (8.7) and Clinical Pharmacology (12.3)].

5.19 Risks of Gastrointestinal Complications

Fentanyl transdermal system is contraindicated in patients with known or suspected gastrointestinal obstruction, including paralytic ileus.

The fentanyl in fentanyl transdermal system may cause spasm of the sphincter of Oddi. Opioids may cause increases in serum amylase. Regularly evaluate patients with biliary tract disease, including acute pancreatitis for worsening symptoms.

Cases of opioid-induced esophageal dysfunction (OIED) have been reported in patients taking opioids. The risk of OIED may increase as the dose and/or duration of opioids increases. Regularly evaluate patients for signs and symptoms of OIED (e.g., dysphagia, regurgitation, non-cardiac chest pain), and if necessary, adjust opioid therapy as clinically appropriate [see Clinical Pharmacology (12.2)].

5.20 Increased Risk of Seizures in Patients with Seizure Disorders

The fentanyl in fentanyl transdermal system may increase the frequency of seizures in patients with seizure disorders, and may increase the risk of seizures occurring in other clinical settings associated with seizures. Regularly evaluate patients with a history of seizure disorders for worsened seizure control during fentanyl transdermal system therapy.

5.21 Withdrawal

Do not rapidly reduce or abruptly discontinue fentanyl transdermal system in a patient physically dependent on opioids. When discontinuing fentanyl transdermal system in a physically dependent patient, gradually taper the dosage. Rapid tapering of fentanyl transdermal system in a patient physically dependent on opioids may lead to a withdrawal syndrome and return of pain [see Dosage and Administration (2.9), Drug Abuse and Dependence (9.3)].

Additionally, avoid the use of mixed agonist/antagonist (e.g., pentazocine, nalbuphine, and butorphanol) or partial agonist (e.g., buprenorphine) analgesics in patients who are receiving a full opioid agonist analgesic, including fentanyl transdermal system. In these patients, mixed agonist/antagonist and partial agonist analgesics may reduce the analgesic effect and/or may precipitate withdrawal symptoms [see Drug Interactions (7)].

5.22 Risks of Driving and Operating Machinery

Fentanyl transdermal system may impair the mental or physical abilities required for the performance of potentially dangerous activities, such as driving a car or operating machinery. Warn patients not to drive or operate dangerous machinery unless they are tolerant to the effects of the fentanyl transdermal system and know how they will react to the medication [see Patient Counseling Information (17)].

6 ADVERSE REACTIONS

The following serious adverse reactions are discussed elsewhere in the labeling:

- Addiction, Abuse, and Misuse [see Warnings and Precautions (5.1)]
- Life-Threatening Respiratory Depression [see Warnings and Precautions (5.2)]
- Accidental Exposure [see Warnings and Precautions (5.3)]
- Neonatal Opioid Withdrawal Syndrome [see Warnings and Precautions (5.5)]
- Interactions with Benzodiazepines or Other Central Nervous System Depressants [see Warnings and Precautions (5.4)]
- Opioid-Induced Hyperalgesia and Allodynia [see Warnings and Precautions (5.10)]
- Serotonin Syndrome [see Warnings and Precautions (5.11)]
- Adrenal Insufficiency [see Warnings and Precautions (5.13)]
- Severe Hypotension [see Warnings and Precautions (5.14)]
- Gastrointestinal Adverse Reactions [see Warnings and Precautions (5.19)]
- Seizures [see Warnings and Precautions (5.20)]
- Withdrawal [see Warnings and Precautions (5.21)]

6.1 Clinical Trial Experience

Because clinical trials are conducted under widely varying conditions, adverse reaction rates observed in the clinical trials of a drug cannot be directly compared to rates in the clinical trials of another drug and may not reflect the rates observed in clinical practice.

The safety of fentanyl transdermal system was evaluated in 216 patients who took at least one dose of fentanyl transdermal system in a multicenter, double-blind, randomized, placebo-controlled clinical trial of fentanyl transdermal system. This trial examined patients over 40 years of age with severe pain induced by osteoarthritis of the hip or knee and who were in need of and waiting for joint replacement.

The most common adverse reactions (≥5%) in a double-blind, randomized, placebo-controlled clinical trial in patients with severe pain were nausea, vomiting, somnolence, dizziness, insomnia, constipation, hyperhidrosis, fatigue, feeling cold, and anorexia. Other common adverse reactions (≥5%) reported in clinical trials in patients with chronic malignant or nonmalignant pain were headache and diarrhea. Adverse reactions reported for ≥1% of fentanyl transdermal system-treated patients and with an incidence greater than placebo-treated patients are shown in Table 3.

The most common adverse reactions that were associated with discontinuation in patients with pain (causing discontinuation in ≥1% of patients) were depression, dizziness, somnolence, headache, nausea, vomiting, constipation, hyperhidrosis, and fatigue.

Table 3. Adverse Reactions Reported by ≥1% of Fentanyl Transdermal System-treated Patients and With an Incidence Greater Than Placebo-treated Patients in 1 Double-Blind, Placebo-Controlled Clinical Trial of Fentanyl Transdermal System
System/Organ ClassAdverse Reaction | Fentanyl Transdermal System%(N=216) | Placebo%(N=200)
Cardiac disorders
Palpitations | 4 | 1
Ear and labyrinth disorders
Vertigo | 2 | 1
Gastrointestinal disorders
Nausea | 41 | 17
Vomiting | 26 | 3
Constipation | 9 | 1
Abdominal pain upper | 3 | 2
Dry mouth | 2 | 0
General disorders and administration site conditions
Fatigue | 6 | 3
Feeling cold | 6 | 2
Malaise | 4 | 1
Asthenia | 2 | 0
Edema peripheral | 1 | 1
Metabolism and nutrition disorders
Anorexia | 5 | 0
Musculoskeletal and connective tissue disorders
Muscle spasms | 4 | 2
Nervous system disorders
Somnolence | 19 | 3
Dizziness | 10 | 4
Psychiatric disorders
Insomnia | 10 | 7
Depression | 1 | 0
Skin and subcutaneous tissue disorders
Hyperhidrosis | 6 | 1
Pruritus | 3 | 2
Rash | 2 | 1

Adverse reactions not reported in Table 3 that were reported by ≥1% of fentanyl transdermal system-treated adult and pediatric patients (N=1854) in 11 controlled and uncontrolled clinical trials of fentanyl transdermal system used for the treatment of chronic malignant or nonmalignant pain are shown in Table 4.

Table 4. Adverse Reactions Reported by ≥1% of Fentanyl Transdermal System-treated Patients in 11 Clinical Trials of Fentanyl Transdermal System
System/Organ Class Adverse Reaction | Fentanyl Transdermal System % (N=1854)
Gastrointestinal disorders
Diarrhea | 10
Abdominal pain | 3
Immune system disorders
Hypersensitivity | 1
Nervous system disorders
Headache | 12
Tremor | 3
Paresthesia | 2
Psychiatric disorders
Anxiety | 3
Confusional state | 2
Hallucination | 1
Renal and urinary disorders
Urinary retention | 1
Skin and subcutaneous tissue disorders
Erythema | 1

The following adverse reactions occurred in adult and pediatric patients with an overall frequency of <1% and are listed in descending frequency within each System/Organ Class:

Cardiac disorders: cyanosis

Eye disorders: miosis

Gastrointestinal disorders: subileus

General disorders and administration site conditions: application site reaction, influenza-like illness, application site hypersensitivity, drug withdrawal syndrome, application site dermatitis

Musculoskeletal and connective tissue disorders: muscle twitching

Nervous system disorders: hypoesthesia

Psychiatric disorders: disorientation, euphoric mood

Reproductive system and breast disorders: erectile dysfunction, sexual dysfunction

Respiratory, thoracic and mediastinal disorders: respiratory depression

Skin and subcutaneous tissue disorders: eczema, dermatitis allergic, dermatitis contact

Pediatrics

The safety of fentanyl transdermal system was evaluated in three open-label trials in 289 pediatric patients with chronic pain, 2 years of age through 18 years of age. Adverse reactions reported by ≥1% of fentanyl transdermal system-treated pediatric patients are shown in Table 5.

Table 5. Adverse Reactions Reported by ≥1% of Fentanyl Transdermal System-treated Pediatric Patients in 3 Clinical Trials of Fentanyl Transdermal System
System/Organ Class Adverse Reaction | Fentanyl Transdermal System % (N=289)
Gastrointestinal disorders
Vomiting | 34
Nausea | 24
Constipation | 13
Diarrhea | 13
Abdominal pain | 9
Abdominal pain upper | 4
Dry mouth | 2
General disorders and administration site conditions
Edema peripheral | 5
Fatigue | 2
Application site reaction | 1
Asthenia | 1
Immune system disorders
Hypersensitivity | 3
Metabolism and nutrition disorders
Anorexia | 4
Musculoskeletal and connective tissue disorders
Muscle spasms | 2
Nervous system disorders
Headache | 16
Somnolence | 5
Dizziness | 2
Tremor | 2
Hypoesthesia | 1
Psychiatric disorders
Insomnia | 6
Anxiety | 4
Depression | 2
Hallucination | 2
Renal and urinary disorders
Urinary retention | 3
Respiratory, thoracic and mediastinal disorders
Respiratory depression | 1
Skin and subcutaneous tissue disorders
Pruritus | 13
Rash | 6
Hyperhidrosis | 3
Erythema | 3

6.2 Postmarketing Experience

The following adverse reactions have been identified during post-approval use of fentanyl transdermal system. Because these reactions are reported voluntarily from a population of uncertain size, it is not always possible to reliably estimate their frequency or establish a causal relationship to drug exposure.

Cardiac Disorders: tachycardia, bradycardia

Eye Disorders: vision blurred

Gastrointestinal Disorders: ileus, dyspepsia

General Disorders and Administration Site Conditions: pyrexia, application site erosion and application site ulcer

Investigations: weight decreased

Nervous System Disorders: convulsions (including clonic convulsions and grand mal convulsion), amnesia, depressed level of consciousness, loss of consciousness

Psychiatric Disorders: agitation

Respiratory, Thoracic, and Mediastinal Disorders: respiratory distress, apnea, bradypnea, hypoventilation, dyspnea

Vascular Disorders: hypotension, hypertension

Serotonin syndrome: Cases of serotonin syndrome, a potentially life-threatening condition, have been reported during concomitant use of opioids with serotonergic drugs.

Adrenal insufficiency: Cases of adrenal insufficiency have been reported with opioid use, more often following greater than one month of use.

Anaphylaxis: Anaphylaxis, including anaphylactic shock, has been reported with ingredients contained in fentanyl transdermal system.

Androgen deficiency: Cases of androgen deficiency have occurred with use of opioids for an extended period of time [see Clinical Pharmacology (12.2)].

Hyperalgesia and Allodynia: Cases of hyperalgesia and allodynia have been reported with opioid therapy of any duration [see Warnings and Precautions (5.10)].

Hypoglycemia: Cases of hypoglycemia have been reported in patients taking opioids. Most reports were in patients with at least one predisposing risk factor (e.g., diabetes).

Opioid-induced esophageal dysfunction (OIED): Cases of OIED have been reported in patients taking opioids, and may occur more frequently in patients taking higher doses of opioids, and/or in patients taking opioids longer term [see Warnings and Precautions (5.19)].

Adverse Reactions from Observational Studies

A prospective, observational cohort study estimated the risks of addiction, abuse, and misuse in patients initiating long-term use of Schedule II opioid analgesics between 2017 and 2021. Study participants included in one or more analyses had been enrolled in selected insurance plans or health systems for at least one year, were free of at least one outcome at baseline, completed a minimum number of follow-up assessments, and either: 1) filled multiple extended-release/long-acting opioid analgesic prescriptions during a 90-day period (n=978); or 2) filled any Schedule II opioid analgesic prescriptions covering at least 70 of 90 days (n=1,244). Those included also had no dispensing of the qualifying opioids in the previous 6 months.

Over 12 months:

- approximately 1% to 6% of participants across the two cohorts newly met criteria for addiction, as assessed with two validated interview-based measures of moderate-to-severe opioid use disorder based on Diagnostic and Statistical Manual of Mental Disorders, Fifth Edition (DSM-5) criteria, and
- approximately 9% and 22% of participants across the two cohorts newly met criteria for prescription opioid abuse and misuse [defined in Drug Abuse and Dependence (9.2)], respectively, as measured with a validated self-reported instrument.

A retrospective, observational cohort study estimated the risk of opioid-involved overdose or opioid overdose-related death in patients with new long-term use of Schedule II opioid analgesics from 2006 through 2016 (n=220,249). Included patients had been enrolled in either one of two commercial insurance programs, one managed care program, or one Medicaid program for at least 9 months. New long-term use was defined as having Schedule II opioid analgesic prescriptions covering at least 70 days’ supply over the 3 months prior to study entry and none during the preceding 6 months. Patients were excluded if they had an opioid-involved overdose in the 9 months prior to study entry. Overdose was measured using a validated medical code-based algorithm with linkage to the National Death Index database. The 5-year cumulative incidence estimates for opioid-involved overdose or opioid overdose-related death ranged from approximately 1.5% to 4% across study sites, counting only the first event during follow-up. Approximately 17% of first opioid overdoses observed over the entire study period (5-11 years, depending on the study site) were fatal. Higher baseline opioid dose was the strongest and most consistent predictor of opioid-involved overdose or opioid overdose-related death. Study exclusion criteria may have selected patients at lower risk of overdose, and substantial loss to follow-up (approximately 80%) also may have biased estimates.

The risk estimates from the studies described above may not be generalizable to all patients receiving opioid analgesics, such as those with exposures shorter or longer than the duration evaluated in the studies.

7 DRUG INTERACTIONS

Table 6 includes clinically significant drug interactions with fentanyl transdermal system.

Table 6. Clinically Significant Drug Interactions with Fentanyl Transdermal System

Inhibitors of CYP3A4
Clinical Impact: | The concomitant use of fentanyl transdermal system and CYP3A4 inhibitors can increase the plasma concentration of fentanyl, resulting in increased or prolonged opioid effects particularly when an inhibitor is added after a stable dose of fentanyl transdermal system is achieved [see Warnings and Precautions (5.7)].; After stopping a CYP3A4 inhibitor, as the effects of the inhibitor decline, the fentanyl transdermal system plasma concentration will decrease [see Clinical Pharmacology (12.3)], resulting in decreased opioid efficacy or a withdrawal syndrome in patients who had developed physical dependence to fentanyl.
Intervention: | If concomitant use is necessary, consider dosage reduction of fentanyl transdermal system until stable drug effects are achieved. Evaluate patients at frequent intervals for respiratory depression and sedation.; If a CYP3A4 inhibitor is discontinued, consider increasing the fentanyl transdermal system dosage until stable drug effects are achieved. Evaluate for signs of opioid withdrawal.
Examples: | Macrolide antibiotics (e.g., erythromycin), azole-antifungal agents (e.g., ketoconazole), protease inhibitors (e.g., ritonavir), grapefruit juice
CYP3A4 Inducers
Clinical Impact: | The concomitant use of fentanyl transdermal system and CYP3A4 inducers can decrease the plasma concentration of fentanyl [see Clinical Pharmacology (12.3)], resulting in decreased efficacy or onset of a withdrawal syndrome in patients who have developed physical dependence to fentanyl [see Warnings and Precautions (5.7)].; After stopping a CYP3A4 inducer, as the effects of the inducer decline, the fentanyl plasma concentration will increase [see Clinical Pharmacology (12.3)], which could increase or prolong both the therapeutic effects and adverse reactions, and may cause serious respiratory depression.
Intervention: | If concomitant use is necessary, consider increasing the fentanyl transdermal system dosage until stable drug effects are achieved. Evaluate for signs of opioid withdrawal. If a CYP3A4 inducer is discontinued, consider fentanyl transdermal system dosage reduction and evaluate patients at frequent intervals for signs of respiratory depression and sedation.
Examples: | Rifampin, carbamazepine, phenytoin
Benzodiazepines and Other Central Nervous System (CNS) Depressants
Clinical Impact: | Due to additive pharmacologic effect, the concomitant use of benzodiazepines or other CNS depressants, including alcohol, can increase the risk of hypotension, respiratory depression, profound sedation, coma, and death.
Intervention: | Reserve concomitant prescribing of these drugs for use in patients for whom alternative treatment options are inadequate. Limit dosages and durations to the minimum required. Inform patients and caregivers of this potential interaction, educate them on the signs and symptoms of respiratory depression (including sedation). If concomitant use is warranted, consider recommending or prescribing an opioid overdose reversal agent [see Dosage and Administration (2.2), Warnings and Precautions (5.1, 5.2, 5.4)].
Examples: | Benzodiazepines and other sedatives/hypnotics, anxiolytics, tranquilizers, muscle relaxants, general anesthetics, antipsychotics, gabapentinoids (gabapentin or pregabalin), other opioids, alcohol.
Serotonergic Drugs
Clinical Impact: | The concomitant use of opioids with other drugs that affect the serotonergic neurotransmitter system has resulted in serotonin syndrome [see Warnings and Precautions (5.11)].
Intervention: | If concomitant use is warranted, frequently evaluate the patient, particularly during treatment initiation and dose adjustment. Discontinue fentanyl transdermal system if serotonin syndrome is suspected.
Examples: | Selective serotonin reuptake inhibitors (SSRIs), serotonin and norepinephrine reuptake inhibitors (SNRIs), tricyclic antidepressants (TCAs), triptans, 5-HT3 receptor antagonists, drugs that affect the serotonin neurotransmitter system (e.g., mirtazapine, trazodone, tramadol), certain muscle relaxants (i.e., cyclobenzaprine, metaxalone), monoamine oxidase (MAO) inhibitors (those intended to treat psychiatric disorders and also others, such as linezolid and intravenous methylene blue).
Monoamine Oxidase Inhibitors (MAOIs)
Clinical Impact: | MAOI interactions with opioids may manifest as serotonin syndrome [see Warnings and Precautions (5.11)] or opioid toxicity (e.g., respiratory depression, coma).
Intervention: | The use of fentanyl transdermal system is not recommended for patients taking MAOIs or within 14 days of stopping such treatment.
Examples: | phenelzine, tranylcypromine, linezolid
Mixed Agonist/Antagonist and Partial Agonist Opioid Analgesics
Clinical Impact: | May reduce the analgesic effect of fentanyl transdermal system and/or precipitate withdrawal symptoms.
Intervention: | Avoid concomitant use.
Examples: | butorphanol, nalbuphine, pentazocine, buprenorphine
Muscle Relaxants
Clinical Impact: | Fentanyl transdermal system may enhance the neuromuscular blocking action of skeletal muscle relaxants and produce an increased degree of respiratory depression.
Intervention: | Because respiratory depression may be greater than otherwise expected, decrease the dosage of fentanyl transdermal system and/or the muscle relaxant as necessary. Due to the risk of respiratory depression with concomitant use of skeletal muscle relaxants and opioids, consider recommending or prescribing an opioid overdose reversal agent [see Dosage and Administration (2.2), Warnings and Precautions (5.2, 5.4)].
Examples: | cyclobenzaprine, metaxalone
Diuretics
Clinical Impact: | Opioids can reduce the efficacy of diuretics by inducing the release of antidiuretic hormone.
Intervention: | Evaluate patients for signs of diminished diuresis and/or effects on blood pressure and increase the dosage of the diuretic as needed.
Anticholinergic Drugs
Clinical Impact: | The concomitant use of anticholinergic drugs may increase risk of urinary retention and/or severe constipation, which may lead to paralytic ileus.
Intervention: | Evaluate patients for signs of urinary retention or reduced gastric motility when fentanyl transdermal system is used concomitantly with anticholinergic drugs.

8 USE IN SPECIFIC POPULATIONS

8.1 Pregnancy

Risk Summary
Use of opioid analgesics for an extended period of time during pregnancy may cause neonatal opioid withdrawal syndrome [see Warnings and Precautions (5.5)]. Available data with fentanyl transdermal system in pregnant women are insufficient to inform a drug-associated risk for major birth defects and miscarriage.

In animal reproduction studies, fentanyl administration to pregnant rats during organogenesis was embryocidal at doses within the range of the human recommended dosing. When administered during gestation through lactation fentanyl administration to pregnant rats resulted in reduced pup survival and developmental delays at doses within the range of the human recommended dosing. No evidence of malformations were noted in animal studies completed to date [see Data].

The estimated background risk of major birth defects and miscarriage for the indicated population is unknown. All pregnancies have a background risk of birth defect, loss, or other adverse outcomes. In the U.S. general population, the estimated background risk of major birth defects and miscarriage in clinically recognized pregnancies is 2 to 4% and 15 to 20%, respectively.

Clinical Considerations
Fetal/Neonatal Adverse Reactions
Use of opioid analgesics for an extended period of time during pregnancy for medical or nonmedical purposes can result in physical dependence in the neonate and neonatal opioid withdrawal syndrome shortly after birth. Neonatal opioid withdrawal syndrome presents as irritability, hyperactivity and abnormal sleep pattern, high pitched cry, tremor, vomiting, diarrhea, and failure to gain weight. The onset, duration, and severity of neonatal opioid withdrawal syndrome vary based on the specific opioid used, duration of use, timing and amount of last maternal use, and rate of elimination of the drug by the newborn. Observe newborns for symptoms of neonatal opioid withdrawal syndrome and manage accordingly [see Warnings and Precautions (5.5)].

Labor or Delivery

Opioids cross the placenta and may produce respiratory depression and psycho-physiologic effects in neonates. An opioid overdose reversal agent, such as naloxone or nalmefene, must be available for reversal of opioid-induced respiratory depression in the neonate. Fentanyl transdermal system is not recommended for use in pregnant women during or immediately prior to labor, when use of shorter-acting analgesics or other analgesic techniques are more appropriate. Opioid analgesics, including fentanyl transdermal system, can prolong labor through actions that temporarily reduce the strength, duration, and frequency of uterine contractions. However, this effect is not consistent and may be offset by an increased rate of cervical dilatation, which tends to shorten labor. Monitor neonates exposed to opioid analgesics during labor for signs of excess sedation and respiratory depression.

Data
Human Data
There are no adequate and well-controlled studies in pregnant women. Fentanyl transdermal system should be used during pregnancy only if the potential benefit justifies the potential risk to the fetus.

Chronic maternal treatment with fentanyl during pregnancy has been associated with transient respiratory depression, behavioral changes, or seizures characteristic of neonatal abstinence syndrome in newborn infants. Symptoms of neonatal respiratory or neurological depression were no more frequent than expected in most studies of infants born to women treated acutely during labor with intravenous or epidural fentanyl. Transient neonatal muscular rigidity has been observed in infants whose mothers were treated with intravenous fentanyl.

Animal Data
No evidence of malformations or adverse effects on the fetus was reported in a published study in which pregnant rats were administered fentanyl continuously via subcutaneously implanted osmotic minipumps at doses of 10, 100, or 500 mcg/kg/day starting 2 weeks prior to breeding and throughout pregnancy. The high dose was approximately 2 times the daily human dose administered by a 100 mcg/hr patch on a mg/m^2 basis).

In contrast, the intravenous administration of fentanyl (0, 0.01, or 0.03 mg/kg) to pregnant rats from Gestation Day 6 to 18 suggested evidence of embryo-toxicity and a slight increase in mean delivery time in the 0.03 mg/kg/day group (0.1 times the human dose administered by a 100 mcg/hr patch on a mg/m^2 basis). There was no clear evidence of teratogenicity noted.

Pregnant female New Zealand White rabbits were treated with fentanyl (0, 0.025, 0.1, 0.4 mg/kg) via intravenous infusion from day 6 to day 18 of pregnancy. Fentanyl produced a slight decrease in the body weight of the live fetuses at the high dose, which may be attributed to maternal toxicity. Under the conditions of the assay, there was no evidence for fentanyl induced adverse effects on embryo-fetal development at doses up to 0.4 mg/kg (approximately 3 times the daily human dose administered by a 100 mcg/hr patch on a mg/m^2 basis).

The potential effects of fentanyl on prenatal and postnatal development were examined in the rat model. Female Wistar rats were treated with 0, 0.025, 0.1, or 0.4 mg/kg/day fentanyl via intravenous infusion from day 6 of pregnancy through 3 weeks of lactation. Fentanyl treatment (0.4 mg/kg/day) significantly decreased body weight in male and female pups and also decreased survival in pups at day 4. Both the mid-dose and high-dose of fentanyl animals demonstrated alterations in some physical landmarks of development (delayed incisor eruption and eye opening) and transient behavioral development (decreased locomotor activity at day 28 which recovered by day 50). The mid-dose and the high-dose are 0.4 and 1.6 times the daily human dose administered by a 100 mcg/hr patch on a mg/m^2 basis.

8.2 Lactation

Risk Summary
Fentanyl is excreted in human milk; therefore, fentanyl transdermal system is not recommended for use in nursing women because of the possibility of effects in their infants.

Because of the potential for serious adverse reactions, including excess sedation and respiratory depression in a breastfed infant, advise patients that breastfeeding is not recommended during treatment with fentanyl transdermal system.

Clinical Considerations
Monitor infants exposed to fentanyl transdermal system through breast milk for excess sedation and respiratory depression. Withdrawal symptoms can occur in breastfed infants when maternal administration of an opioid analgesic is stopped, or when breast-feeding is stopped.

8.3 Females and Males of Reproductive Potential

Infertility
Use of opioids for an extended period of time may cause reduced fertility in females and males of reproductive potential. It is not known whether these effects on fertility are reversible [see Adverse Reactions (6.2), Clinical Pharmacology (12.2), Nonclinical Toxicology (13.1)].

8.4 Pediatric Use

The safety of fentanyl transdermal system was evaluated in three open-label trials in 289 pediatric patients with chronic pain, 2 years of age through 18 years of age. Starting doses of 25 mcg/hr and higher were used by 181 patients who had been on prior daily opioid doses of at least 45 mg/day of oral morphine or an equianalgesic dose of another opioid. Initiation of fentanyl transdermal system therapy in pediatric patients taking less than 60 mg/day of oral morphine or an equianalgesic dose of another opioid has not been evaluated in controlled clinical trials.

The safety and effectiveness of fentanyl transdermal system in children under 2 years of age have not been established.

To guard against excessive exposure to fentanyl transdermal system by young children, advise caregivers to strictly adhere to recommended fentanyl transdermal system application and disposal instructions [see Dosage and Administration (2.7), (2.8) and Warnings and Precautions (5.3)].

8.5 Geriatric Use

Clinical studies of fentanyl transdermal system did not include sufficient numbers of subjects aged 65 and over to determine whether they respond differently from younger subjects. Other reported clinical experience has not identified differences in responses between the elderly and younger patients. In general, use caution when selecting a dosage for an elderly patient, usually starting at the low end of the dosing range, reflecting the greater frequency of decreased hepatic, renal, or cardiac function, and of concomitant disease or other drug therapy.

Data from intravenous studies with fentanyl suggest that the elderly patients may have reduced clearance and a prolonged half-life. Moreover, elderly patients may be more sensitive to the active substance than younger patients. A study conducted with the fentanyl transdermal system in elderly patients demonstrated that fentanyl pharmacokinetics did not differ significantly from young adult subjects, although peak serum concentrations tended to be lower and mean half-life values were prolonged to approximately 34 hours [see Clinical Pharmacology (12.3)].

Respiratory depression is the chief risk for elderly patients treated with opioids, and has occurred after large initial doses were administered to patients who were not opioid-tolerant or when opioids were co-administered with other agents that depress respiration. Titrate the dosage of fentanyl transdermal system slowly in geriatric patients and frequently reevaluate the patient for signs of central nervous system and respiratory depression [see Warnings and Precautions (5.12)].

Fentanyl is known to be substantially excreted by the kidney, and the risk of adverse reactions to this drug may be greater in patients with impaired renal function. Because elderly patients are more likely to have decreased renal function, care should be taken in dose selection, and it may be useful to regularly evaluate renal function.

8.6 Hepatic Impairment

The effect of hepatic impairment on the pharmacokinetics of fentanyl transdermal system has not been fully evaluated. A clinical pharmacology study with fentanyl transdermal system in patients with cirrhosis has shown that systemic fentanyl exposure increased in these patients. Because there is in-vitro and in-vivo evidence of extensive hepatic contribution to the elimination of fentanyl transdermal system, hepatic impairment would be expected to have significant effects on the pharmacokinetics of fentanyl transdermal system. Avoid use of fentanyl transdermal system in patients with severe hepatic impairment [see Dosage and Administration (2.5), Warnings and Precautions (5.17) and Clinical Pharmacology (12.3)].

8.7 Renal Impairment

The effect of renal impairment on the pharmacokinetics of fentanyl transdermal system has not been fully evaluated. A clinical pharmacology study with intravenous fentanyl in patients undergoing kidney transplantation has shown that patients with high blood urea nitrogen level had low fentanyl clearance. Because there is in-vivo evidence of renal contribution to the elimination of fentanyl transdermal system, renal impairment would be expected to have significant effects on the pharmacokinetics of fentanyl transdermal system. Avoid the use of fentanyl transdermal system in patients with severe renal impairment [see Dosage and Administration (2.6), Warnings and Precautions (5.18) and Clinical Pharmacology (12.3)].

9 DRUG ABUSE AND DEPENDENCE

9.1 Controlled Substance

Fentanyl transdermal system contains fentanyl, a Schedule II controlled substance.

9.2 Abuse

Fentanyl transdermal system contains fentanyl, a substance with high potential for misuse and abuse, which can lead to the development of substance use disorder, including addiction [see Warnings and Precautions (5.1)].

Misuse is the intentional use, for therapeutic purposes, of a drug by an individual in a way other than prescribed by a healthcare provider or for whom it was not prescribed.

Abuse is the intentional, non-therapeutic use of a drug, even once, for its desirable psychological or physiological effects.

Drug addiction is a cluster of behavioral, cognitive, and physiological phenomena that may include a strong desire to take the drug, difficulties in controlling drug use (e.g., continuing drug use despite harmful consequences, giving a higher priority to drug use than other activities and obligations), and possible tolerance or physical dependence.

Misuse and abuse of fentanyl transdermal system increases risk of overdose, which may lead to central nervous system and respiratory depression, hypotension, seizures, and death. The risk is increased with concurrent abuse of fentanyl transdermal system with alcohol and other CNS depressants. Abuse of and addiction to opioids in some individuals may not be accompanied by concurrent tolerance and symptoms of physical dependence. In addition, abuse of opioids can occur in the absence of addiction.

All patients treated with opioids require careful and frequent reevaluation for signs of misuse, abuse, and addiction, because use of opioid analgesic products carries the risk of addiction even under appropriate medical use. Patients at high risk of fentanyl transdermal system abuse include those with a history of prolonged use of any opioid, including products containing fentanyl, those with a history of drug or alcohol abuse, or those who use fentanyl transdermal system in combination with other abused drugs.

“Drug-seeking” behavior is very common in persons with substance use disorders. Drug-seeking tactics include emergency calls or visits near the end of office hours, refusal to undergo appropriate examination, testing, or referral, repeated “loss” of prescriptions, tampering with prescriptions, and reluctance to provide prior medical records or contact information for other treating healthcare provider(s). “Doctor shopping” (visiting multiple prescribers to obtain additional prescriptions) is common among people who abuse drugs and people with substance use disorder. Preoccupation with achieving adequate pain relief can be appropriate behavior in a patient with inadequate pain control.

Fentanyl transdermal system, like other opioids, can be diverted for nonmedical use into illicit channels of distribution. Careful record-keeping of prescribing information, including quantity, frequency, and renewal requests, as required by state and federal law, is strongly advised.

Proper assessment of the patient, proper prescribing practices, periodic reevaluation of therapy, and proper dispensing and storage are appropriate measures that help to limit abuse of opioid drugs.

Risks Specific to the Abuse of Fentanyl Transdermal System
Fentanyl transdermal system is intended for transdermal use only. Abuse of fentanyl transdermal system poses a risk of overdose and death. This risk is increased with concurrent use of fentanyl transdermal system with alcohol and/or other CNS depressants [see Warnings and Precautions (5.4), and Drug Interactions (7)]. Intentional compromise of the transdermal delivery system may result in the uncontrolled delivery of fentanyl and pose a significant risk to the abuser that could result in overdose and death [see Warnings and Precautions (5.1)]. Abuse may occur by applying the transdermal system in the absence of legitimate purpose, or by swallowing, snorting or injecting fentanyl extracted from the transdermal system.

9.3 Dependence

Both tolerance and physical dependence can develop during use of opioid therapy.

Tolerance is a physiological state characterized by a reduced response to a drug after repeated administration (i.e., a higher dose of a drug is required to produce the same effect that was once obtained at a lower dose).

Physical dependence is a state that develops as a result of a physiological adaptation in response to repeated drug use, manifested by withdrawal signs and symptoms after abrupt discontinuation or a significant dose reduction of a drug.

Withdrawal may be precipitated through the administration of drugs with opioid antagonist activity (e.g., naloxone, nalmefene), mixed agonist/antagonist analgesics (e.g., pentazocine, butorphanol, nalbuphine), or partial agonists (e.g., buprenorphine). Physical dependence may not occur to a clinically significant degree until after several days to weeks of continued use.

Do not rapidly reduce or abruptly discontinue fentanyl transdermal system in a patient physically dependent on opioids. Rapid reduction or abrupt discontinuation of fentanyl transdermal system in a patient physically dependent on opioids may lead to serious withdrawal symptoms, uncontrolled pain, and suicide. Rapid reduction or abrupt discontinuation has also been associated with attempts to find other sources of opioid analgesics, which may be confused with drug-seeking for abuse.

When discontinuing fentanyl transdermal system, gradually taper the dosage using a patient-specific plan that considers the following: the dose of fentanyl transdermal system the patient has been taking, the duration of treatment, and the physical and psychological attributes of the patient. To improve the likelihood of a successful taper and minimize withdrawal symptoms, it is important that the opioid tapering schedule is agreed upon by the patient. In patients taking opioids for an extended period of time at high doses, ensure that a multimodal approach to pain management, including mental health support (if needed), is in place prior to initiating an opioid analgesic taper [see Dosage and Administration (2.9), and Warnings and Precautions (5.21)].

Infants born to mothers physically dependent on opioids will also be physically dependent and may exhibit respiratory difficulties and withdrawal signs [see Use in Specific Populations (8.1)].

10 OVERDOSAGE

Clinical Presentation
Acute overdose with fentanyl transdermal system can be manifested by respiratory depression, somnolence progressing to stupor or coma, skeletal muscle flaccidity, cold and clammy skin, constricted pupils, and, in some cases, pulmonary edema, bradycardia, hypotension, hypoglycemia, partial or complete airway obstruction, atypical snoring, and death. Marked mydriasis rather than miosis may be seen with hypoxia in overdose situations [see Clinical Pharmacology (12.2)]. Toxic leukoencephalopathy has been reported after opioid overdose and can present hours, days, or weeks after apparent recovery from the initial intoxication.

Treatment of Overdose

Give primary attention to the reestablishment of a patent airway and institution of assisted or controlled ventilation, if needed. Employ other supportive measures (including oxygen and vasopressors) in the management of circulatory shock and pulmonary edema as indicated. Cardiac arrest or arrhythmias will require advanced life support measures. Once stable, examine the patient and ensure that all fentanyl transdermal systems have been removed.

For clinically significant respiratory or circulatory depression secondary to opioid overdose, administer an opioid overdose reversal agent such as naloxone or nalmefene.

Because the duration of opioid reversal is expected to be less than the duration of action of fentanyl in fentanyl transdermal systems, carefully monitor the patient until spontaneous respiration is reliably reestablished. After fentanyl transdermal system removal, serum fentanyl concentrations decline gradually, falling about 50% in approximately 20 to 27 hours. Therefore, management of an overdose must be monitored accordingly, at least 72 to 96 hours beyond the overdose.

In an individual physically dependent on opioids, administration of the recommended usual dosage of the opioid overdose reversal agent will precipitate an acute withdrawal syndrome. The severity of the withdrawal symptoms experienced will depend on the degree of physical dependence and the dose of the reversal agent administered. If a decision is made to treat serious respiratory depression in the physically-dependent patient, administration of the reversal agent should be initiated with care and by titration with smaller than usual doses of the reversal agent.

11 DESCRIPTION

Fentanyl transdermal system contains fentanyl, an opioid agonist, available as a patch for transdermal administration. The amount of fentanyl released from each system per hour is proportional to the surface area (25 mcg/hr per 7.8 cm^2). The composition per unit area of all system sizes is identical.

Strength (mcg/hr) | Size (cm^2) | Fentanyl Content (mg) | Color of Printing on Back of Patch
12 [Nominal delivery rate is 12.5 mcg/hr] | 3.9 | 1.375 | Green
25 [Nominal delivery rate per hour] | 7.8 | 2.75 | Green
37.5 | 11.7 | 4.125 | Green
50 | 15.6 | 5.50 | Green
62.5 | 19.6 | 6.875 | Green
75 | 23.4 | 8.25 | Green
100 | 31.3 | 11.0 | Green

The n‑octanol: water partition coefficient is 860:1. The pKa is 8.4.

The chemical name is N-Phenyl-N-(1-(2-phenylethyl)-4-piperidinyl) propanamide. The structural formula is:

Fentanyl transdermal systems are a rectangular, opaque patch with rounded corners:

- 12 mcg/hr: Fentanyl Transdermal System 12 mcg/hr printed in green
- 25 mcg/hr: Fentanyl Transdermal System 25 mcg/hr printed in green
- 37.5 mcg/hr: Fentanyl Transdermal System 37.5 mcg/hr printed in green
- 50 mcg/hr: Fentanyl Transdermal System 50 mcg/hr printed in green
- 62.5 mcg/hr: Fentanyl Transdermal System 62.5 mcg/hr printed in green
- 75 mcg/hr: Fentanyl Transdermal System 75 mcg/hr printed in green
- 100 mcg/hr: Fentanyl Transdermal System 100 mcg/hr printed in green

The 12 mcg/hour system has a green border and the 25, 37.5, 50, 62.5, 75 and 100 mcg/hour systems have green stripes that increase in number with each sequential increasing dosage strength.

Fentanyl transdermal system is a rectangular opaque unit comprising a protective liner and four functional layers. Proceeding from the outer surface toward the surface adhering to skin, these layers are:

1) a backing layer of PET foil;

2) a drug containing layer of fentanyl and dipropylene glycol with hydroxypropyl cellulose;

3) an ethylene vinyl-acetate copolymer membrane that controls the rate of fentanyl delivery to the skin surface; and

4) a silicone adhesive. Before use, a protective liner covering the adhesive layer is removed and discarded.

12 CLINICAL PHARMACOLOGY

12.1 Mechanism of Action

Fentanyl is an opioid agonist. Fentanyl interacts predominately with the opioid mu-receptor. These mu-binding sites are distributed in the human brain, spinal cord, and other tissues.

12.2 Pharmacodynamics

Effects on the Central Nervous System
Fentanyl produces respiratory depression by direct action on brain stem respiratory centers. The respiratory depression involves a reduction in the responsiveness of the brain stem respiratory centers to both increases in carbon dioxide tension and electrical stimulation.

Fentanyl causes miosis, even in total darkness. Pinpoint pupils are a sign of opioid overdose but are not pathognomonic (e.g., pontine lesions of hemorrhagic or ischemic origins may produce similar findings). Marked mydriasis rather than miosis may be seen due to hypoxia in overdose situations.

In clinical trials of 357 non-opioid tolerant subjects treated with fentanyl transdermal system, 13 subjects experienced hypoventilation. Hypoventilation was manifested by respiratory rates of less than 8 breaths/minute or a pCO2 greater than 55 mm Hg. In these studies, the incidence of hypoventilation was higher in nontolerant women (10) than in men (3) and in subjects weighing less than 63 kg (9 of 13). Although subjects with prior impaired respiration were not common in the trials, they had higher rates of hypoventilation. In addition, postmarketing reports have been received that describe opioid-naive post-operative patients who have experienced clinically significant hypoventilation and death with fentanyl transdermal system.

Hypoventilation can occur throughout the therapeutic range of fentanyl serum concentrations, especially for patients who have an underlying pulmonary condition or who receive concomitant opioids or other CNS drugs associated with hypoventilation. The use of fentanyl transdermal system is contraindicated in patients who are not tolerant to opioid therapy.

Effects on the Gastrointestinal Tract and Other Smooth Muscle
Fentanyl causes a reduction in motility associated with an increase in smooth muscle tone in the antrum of the stomach and duodenum. Digestion of food in the small intestine is delayed and propulsive contractions are decreased. Propulsive peristaltic waves in the colon are decreased, while tone is increased to the point of spasm, resulting in constipation. Other opioid-induced effects may include a reduction in biliary and pancreatic secretions, spasm of sphincter of Oddi, transient elevations in serum amylase, and opioid-induced esophageal dysfunction (OIED).

Effects on the Cardiovascular System
Fentanyl produces peripheral vasodilation, which may result in orthostatic hypotension or syncope. Manifestations of histamine release and/or peripheral vasodilation may include pruritus, flushing, red eyes, sweating, and/or orthostatic hypotension.

Histamine assays and skin wheal testing in clinical studies indicate that clinically significant histamine release rarely occurs with fentanyl administration. Clinical assays show no clinically significant histamine release in dosages up to 50 mcg/kg.

Effects on the Endocrine System
Opioids inhibit the secretion of adrenocorticotropic hormone (ACTH), cortisol, and luteinizing hormone (LH) in humans [see Adverse Reactions (6.2)]. They also stimulate prolactin, growth hormone (GH) secretion, and pancreatic secretion of insulin and glucagon.

Use of opioids for an extended period of time may influence the hypothalamic-pituitary-gonadal axis, leading to androgen deficiency that may manifest as low libido, impotence, erectile dysfunction, amenorrhea, or infertility. The causal role of opioids in the clinical syndrome of hypogonadism is unknown because the various medical, physical, lifestyle, and psychological stressors that may influence gonadal hormone levels have not been adequately controlled for in studies conducted to date [see Adverse Reactions (6.2)].

Effects on the Immune System
Opioids have been shown to have a variety of effects on components of the immune system in in vitro and animal models. The clinical significance of these findings is unknown. Overall, the effects of opioids appear to be modestly immunosuppressive.

Concentration-Efficacy Relationships
The minimum effective analgesic concentration will vary widely among patients, especially among patients who have been previously treated with opioid agonists. The minimum effective analgesic concentration of fentanyl for any individual patient may increase over time due to an increase in pain, the development of a new pain syndrome, and/or the development of analgesic tolerance [see Dosage and Administration (2.1, 2.4)].

Concentration-Adverse Reaction Relationships
There is a relationship between increasing fentanyl plasma concentration and increasing frequency of dose-related opioid adverse reactions such as nausea, vomiting, CNS effects, and respiratory depression. In opioid-tolerant patients, the situation may be altered by the development of tolerance to opioid-related adverse reactions [see Dosage and Administration (2.1, 2.3, 2.4)].

12.3 Pharmacokinetics

Absorption
Fentanyl transdermal system is a drug-in-adhesive matrix designed formulation. Fentanyl is released from the matrix at a nearly constant amount per unit time. The concentration gradient existing between the matrix and the lower concentration in the skin drives drug release. Fentanyl moves in the direction of the lower concentration at a rate determined by the matrix and the diffusion of fentanyl through the skin layers. While the actual rate of fentanyl delivery to the skin varies over the 72-hour application period, each system is labeled with a nominal flux which represents the average amount of drug delivered to the systemic circulation per hour across average skin.

While there is variation in dose delivered among patients, the nominal flux of the systems (12.5, 25, 37.5, 50, 62.5, 75, and 100 mcg of fentanyl per hour) is sufficiently accurate as to allow individual titration of dosage for a given patient.

Following fentanyl transdermal system application, the skin under the system absorbs fentanyl, and a depot of fentanyl concentrates in the upper skin layers. Fentanyl then becomes available to the systemic circulation. Serum fentanyl concentrations increase gradually following initial fentanyl transdermal system application, generally leveling off between 12 and 24 hours and remaining relatively constant, with some fluctuation, for the remainder of the 72-hour application period. Peak serum concentrations of fentanyl generally occurred between 20 and 72 hours after initial application (see Table 7). Serum fentanyl concentrations achieved are proportional to the fentanyl transdermal system delivery rate. With continuous use, serum fentanyl concentrations continue to rise for the first two system applications. By the end of the second 72-hour application, a steady-state serum concentration is reached and is maintained during subsequent applications of a patch of the same size (see Figure 1). Patients reach and maintain a steady-state serum concentration that is determined by individual variation in skin permeability and body clearance of fentanyl.

After system removal, serum fentanyl concentrations decline gradually, falling about 50% in approximately 20 to 27 hours. Continued absorption of fentanyl from the skin accounts for a slower disappearance of the drug from the serum than is seen after an IV infusion, where the apparent half-life is approximately 7 (range 3 to 12) hours.

A clinical pharmacology study conducted in healthy adult subjects has shown that the application of heat over the fentanyl transdermal system increased mean overall fentanyl exposure by 120% and average maximum fentanyl level by 61%.

Table 7. Fentanyl Pharmacokinetic Parameters Following First 72-Hour Application of Fentanyl Transdermal System
 | Mean (SD) Time to Maximal Concentration Tmax (hr) | Mean (SD) Maximal Concentration Cmax (ng/mL)
Fentanyl Transdermal System 12 mcg/hr | 28.8 (13.7) | 0.38 (0.13) [Cmax values dose normalized from 4 x 12.5 mcg/hr: Study 2003-038 in healthy volunteers]
Fentanyl Transdermal System 25 mcg/hr | 31.7 (16.5) | 0.85 (0.26) [Cmax values: Study C-2002-048 dose proportionality study in healthy volunteers]
Fentanyl Transdermal System 50 mcg/hr | 32.8 (15.6) | 1.72 (0.53)
Fentanyl Transdermal System 75 mcg/hr | 35.8 (14.1) | 2.32 (0.86)
Fentanyl Transdermal System 100 mcg/hr | 29.9 (13.3) | 3.36 (1.28)

NOTE: After system removal there is continued systemic absorption from residual fentanyl in the skin so that serum concentrations fall 50%, on average, in approximately 20 to 27 hours.

Table 8. Range of Pharmacokinetic Parameters of Intravenous Fentanyl in Patients
 | Clearance (L/hr) Range [70 kg] | Volume of Distribution VSS (L/kg) Range | Half-Life t1/2 (hr) Range
Surgical Patients | 27-75 | 3-8 | 3-12
Hepatically Impaired Patients | 3-80 [Estimated] | 0.8-8 | 4-12
Renally Impaired Patients | 30-78 | – | –

NOTE: Information on volume of distribution and half-life not available for renally impaired patients.

Distribution
Fentanyl plasma protein binding capacity decreases with increasing ionization of the drug. Alterations in pH may affect its distribution between plasma and the central nervous system. Fentanyl accumulates in the skeletal muscle and fat and is released slowly into the blood. The average volume of distribution for fentanyl is 6 L/kg (range 3 to 8; N=8).

Elimination
Metabolism
Fentanyl is metabolized primarily via human cytochrome P450 3A4 isoenzyme system. In humans, the drug appears to be metabolized primarily by oxidative N-dealkylation to norfentanyl and other inactive metabolites that do not contribute materially to the observed activity of the drug.

Skin does not appear to metabolize fentanyl delivered transdermally. This was determined in a human keratinocyte cell assay and in clinical studies in which 92% of the dose delivered from the system was accounted for as unchanged fentanyl that appeared in the systemic circulation.

Excretion
Within 72 hours of IV fentanyl administration, approximately 75% of the dose is excreted in urine, mostly as metabolites with less than 10% representing unchanged drug. Approximately 9% of the dose is recovered in the feces, primarily as metabolites. Mean values for unbound fractions of fentanyl in plasma are estimated to be between 13 and 21%.

Specific Populations
Age: Geriatric Population
Data from intravenous studies with fentanyl suggest that the elderly patients may have reduced clearance and a prolonged half-life. Moreover elderly patients may be more sensitive to the active substance than younger patients. A study conducted with the fentanyl transdermal system in elderly patients demonstrated that fentanyl pharmacokinetics did not differ significantly from young adult subjects, although peak serum concentrations tended to be lower and mean half-life values were prolonged to approximately 34 hours. In this study, a single fentanyl transdermal system 100 mcg/hour patch was applied to a skin site on the upper outer arm in a group of healthy elderly Caucasians ≥65 years old (n=21, mean age 71 years) and worn for 72 hours. The mean Cmax and AUC∞ values were approximately 8% lower and 7% higher, respectively, in the elderly subjects as compared with subjects 18 to 45 years old. Inter-subject variability in AUC∞ was higher in elderly subjects than in healthy adult subjects 18 to 45 years (58% and 37%, respectively). The mean half-life value was longer in subjects ≥65 years old than in subjects 18 to 45 years old (34.4 hours versus 23.5 hours) [see Warnings and Precautions (5.12) and Use in Specific Populations (8.5)].

Age: Pediatric Population
In 1.5 to 5 year old, non-opioid-tolerant pediatric patients, the fentanyl plasma concentrations were approximately twice as high as that of adult patients. In older pediatric patients, the pharmacokinetic parameters were similar to that of adults. However, these findings have been taken into consideration in determining the dosing recommendations for opioid-tolerant pediatric patients (2 years of age and older). For pediatric dosing information, refer to [see Dosage and Administration (2.3)].

Hepatic Impairment
Information on the effect of hepatic impairment on the pharmacokinetics of fentanyl transdermal system is limited. The pharmacokinetics of fentanyl transdermal system delivering 50 mcg/hour of fentanyl for 72 hours was evaluated in patients hospitalized for surgery. Compared to the controlled patients (n=8), Cmax and AUC in the patients with cirrhosis (n=9) increased 35% and 73%, respectively.

Because there is in-vitro and in-vivo evidence of extensive hepatic contribution to the elimination of fentanyl transdermal system, hepatic impairment would be expected to have significant effects on the pharmacokinetics of fentanyl transdermal system. Avoid use of fentanyl transdermal system in patients with severe hepatic impairment [see Dosage and Administration (2.5), Warnings and Precautions (5.17), and Use in Specific Populations (8.6)].

Renal Impairment
Information on the effect of renal impairment on the pharmacokinetics of fentanyl transdermal system is limited. The pharmacokinetics of intravenous injection of 25 mcg/kg fentanyl was evaluated in patients (n=8) undergoing kidney transplantation. An inverse relationship between blood urea nitrogen level and fentanyl clearance was found.

Because there is in-vivo evidence of renal contribution to the elimination of fentanyl transdermal system, renal impairment would be expected to have significant effects on the pharmacokinetics of fentanyl transdermal system. Avoid the use of fentanyl transdermal system in patients with severe renal impairment [see Dosage and Administration (2.6), Warnings and Precautions (5.18) and Use in Specific Populations (8.7)].

Drug Interaction Studies
CYP3A4 Inhibitors
Fentanyl is metabolized mainly via the human cytochrome P450 3A4 isoenzyme system (CYP3A4). The interaction between ritonavir, a CYP3A4 inhibitor, and fentanyl was investigated in eleven healthy volunteers in a randomized crossover study. Subjects received oral ritonavir or placebo for 3 days. The ritonavir dose was 200 mg three times a day on Day 1 and 300 mg three times a day on Day 2 followed by one morning dose of 300 mg on Day 3. On Day 2, fentanyl was given as a single IV dose at 5 mcg/kg two hours after the afternoon dose of oral ritonavir or placebo. Naloxone was administered to counteract the side effects of fentanyl. The results suggested that ritonavir might decrease the clearance of fentanyl by 67%, resulting in a 174% (range 52% to 420%) increase in fentanyl AUC0-∞. The concomitant use of transdermal fentanyl with all CYP3A4 inhibitors (such as ritonavir, ketoconazole, itraconazole, troleandomycin, clarithromycin, nelfinavir, nefazodone, amiodarone, amprenavir, aprepitant, diltiazem, erythromycin, fluconazole, fosamprenavir, verapamil, or grapefruit juice) may result in an increase in fentanyl plasma concentrations, which could increase or prolong adverse drug effects and may cause potentially fatal respiratory depression. Carefully monitor patients receiving fentanyl transdermal system and any CYP3A4 inhibitor for signs of respiratory depression for an extended period of time and adjust the dosage if warranted [see Boxed Warning and Warnings and Precautions (5.7), and Drug Interactions (7)].

CYP3A4 Inducers
Co-administration with agents that induce CYP3A4 activity may reduce the efficacy of fentanyl transdermal system.

13 NONCLINICAL TOXICOLOGY

13.1 Carcinogenesis, Mutagenesis, and Impairment of Fertility

Carcinogenesis
In a two-year carcinogenicity study conducted in rats, fentanyl was not associated with an increased incidence of tumors at subcutaneous doses up to 33 mcg/kg/day in males or
100 mcg/kg/day in females (0.16 and 0.39 times the human daily exposure obtained via the 100 mcg/hr patch based on AUC0-24h comparison).

Mutagenesis
There was no evidence of mutagenicity in the Ames Salmonella mutagenicity assay, the primary rat hepatocyte unscheduled DNA synthesis assay, the BALB/c 3T3 transformation test, and the human lymphocyte and CHO chromosomal aberration in-vitro assays.

Impairment of Fertility
The potential effects of fentanyl on male and female fertility were examined in the rat model via two separate experiments. In the male fertility study, male rats were treated with fentanyl (0, 0.025, 0.1 or 0.4 mg/kg/day) via continuous intravenous infusion for
28 days prior to mating; female rats were not treated. In the female fertility study, female rats were treated with fentanyl (0, 0.025, 0.1 or 0.4 mg/kg/day) via continuous intravenous infusion for 14 days prior to mating until day 16 of pregnancy; male rats were not treated. Analysis of fertility parameters in both studies indicated that an intravenous dose of fentanyl up to 0.4 mg/kg/day to either the male or the female alone produced no effects on fertility (this dose is approximately 1.6 times the daily human dose administered by a 100 mcg/hr patch on a mg/m^2 basis). In a separate study, a single daily bolus dose of fentanyl was shown to impair fertility in rats when given in intravenous doses of 0.3 times the human dose for a period of 12 days.

14 CLINICAL STUDIES

Fentanyl transdermal system as therapy for pain due to cancer has been studied in 153 patients. In this patient population, fentanyl transdermal system has been administered in doses of 25 mcg/hr to 600 mcg/hr. Individual patients have used fentanyl transdermal system continuously for up to 866 days. At one month after initiation of fentanyl transdermal system therapy, patients generally reported lower pain intensity scores as compared to a pre-study analgesic regimen of oral morphine.

The duration of fentanyl transdermal system use varied in cancer patients; 56% of patients used fentanyl transdermal system for over 30 days, 28% continued treatment for more than 4 months, and 10% used fentanyl transdermal system for more than 1 year.

In the pediatric population, the safety of fentanyl transdermal system has been evaluated in 289 patients with chronic pain 2 to 18 years of age. The duration of fentanyl transdermal system use varied; 20% of pediatric patients were treated for ≤ 15 days; 46% for 16 to 30 days; 16% for 31 to 60 days; and 17% for at least 61 days. Twenty-five patients were treated with fentanyl transdermal system for at least 4 months and 9 patients for more than 9 months.

16 HOW SUPPLIED/STORAGE AND HANDLING

Fentanyl transdermal system is supplied in cartons containing 5 individual child-resistant packaged systems. See chart for information regarding individual systems.

Fentanyl Transdermal System Dose (mcg/hr) | System Size (cm^2) | Fentanyl Content (mg) | NDC Number
Fentanyl transdermal system-12 [This lowest strength is designated as 12 mcg/hr (however, the actual strength is 12.5 mcg/hr) to distinguish it from a 125 mcg/hr strength that could be prescribed by using multiple transdermal systems.] | 3.9 | 1.375 | 0406-9112-76
Fentanyl transdermal system-25 | 7.8 | 2.75 | 0406-9125-76
Fentanyl transdermal system-37.5 | 11.7 | 4.125 | 0406-9037-76
Fentanyl transdermal system-50 | 15.6 | 5.50 | 0406-9150-76
Fentanyl transdermal system-62.5 | 19.6 | 6.875 | 0406-9062-76
Fentanyl transdermal system-75 | 23.4 | 8.25 | 0406-9175-76
Fentanyl transdermal system-100 | 31.3 | 11.0 | 0406-9100-76

Store in original unopened pouch. Store up to 25°C (77°F); excursions permitted to 15 to 30°C (59 to 86°F) [see USP Controlled Room Temperature].

Store fentanyl transdermal system securely and dispose of properly [see Patient Counseling Information (17)].

17 PATIENT COUNSELING INFORMATION

Advise the patient to read the FDA-approved patient labeling (Medication Guide and Instructions for Use).

Storage and Disposal
Because of the risks associated with accidental ingestion, misuse, and abuse, advise patients to store fentanyl transdermal system securely, out of sight and reach of children, and in a location not accessible by others, including visitors to the home. Inform patients that leaving fentanyl transdermal system unsecured can pose a deadly risk to others in the home [see Warnings and Precautions (5.1, 5.3), Drug Abuse and Dependence (9.2)].

Advise patients and caregivers that when medicines are no longer needed, they should be disposed of promptly. Expired, unwanted, or unused fentanyl transdermal system should be disposed of by folding the patch so that the adhesive side of the patch adheres to itself, and immediately flushing down the toilet (if a drug take-back option is not readily available) [see Instructions for Use]. Inform patients that they can visit www.fda.gov/drugdisposal for a complete list of medicines recommended for disposal by flushing, as well as additional information on disposal of unused medicines.

Addiction, Abuse, and Misuse
Inform patients that the use of fentanyl transdermal system, even when taken as recommended, can result in addiction, abuse, and misuse, which can lead to overdose and death [see Warnings and Precautions (5.1)]. Instruct patients not to share fentanyl transdermal system with others and to take steps to protect fentanyl transdermal system from theft or misuse.

Life-Threatening Respiratory Depression
Inform patients of the risk of life-threatening respiratory depression, including information that the risk is greatest when starting fentanyl transdermal system or when the dosage is increased, and that it can occur even at recommended dosages.

Educate patients and caregivers on how to recognize respiratory depression and emphasize the importance of calling 911 or getting emergency medical help right away in the event of a known or suspected overdose [see Warnings and Precautions (5.2)].

Accidental Exposure
Inform patients that accidental exposure, especially in children, may result in respiratory depression or death [see Warnings and Precautions (5.3)].

Fentanyl transdermal system can be accidentally transferred to children. Instruct patients to take special precautions to avoid accidental contact when holding or caring for children.

Instruct patients that, if the patch dislodges and accidentally sticks to the skin of another person, to immediately take the patch off, wash the exposed area with water and seek medical attention for the accidentally exposed individual as accidental exposure may lead to death or other serious medical problems.

Interactions with Benzodiazepines and Other CNS Depressants
Inform patients and caregivers that potentially fatal additive effects may occur if fentanyl transdermal system is used with benzodiazepines or other CNS depressants, including alcohol (e.g., non-benzodiazepine sedative/hypnotics, anxiolytics, tranquilizers, muscle relaxants, general anesthetics, antipsychotics, gabapentinoids [gabapentin or pregabalin], and other opioids), and not to use these concomitantly unless supervised by a healthcare provider [see Warnings and Precautions (5.4), Drug Interactions (7)].

Patient Access to an Opioid Overdose Reversal Agent for the Emergency Treatment of Opioid Overdose

Inform patients and caregivers about opioid overdose reversal agents (e.g., naloxone, nalmefene). Discuss the importance of having access to an opioid overdose reversal agent, especially if the patient has risk factors for overdose (e.g., concomitant use of CNS depressants, a history of opioid use disorder, or prior opioid overdose) or if there are household members (including children) or other close contacts at risk for accidental ingestion or opioid overdose.

Discuss with the patient the options for obtaining an opioid overdose reversal agent (e.g., prescription, over-the-counter, or as part of a community-based program) [see Dosage and Administration (2.2), Warnings and Precautions (5.4)].

Educate patients and caregivers on how to recognize the signs and symptoms of an overdose.

Explain to patients and caregivers that effects of opioid overdose reversal agents like naloxone and nalmefene are temporary, and that they must call 911 or get emergency medical help right away in all cases of known or suspected opioid overdose, even if an opioid overdose reversal agent is administered [see Overdosage (10)].

Advise patients and caregivers:

- how to treat with the overdose reversal agent in the event of an opioid overdose.
- to tell family and friends about the opioid overdose reversal agent, and to keep it in a place where family and friends can access it in an emergency.
- to read the Patient Information (or other educational material) that will come with their opioid overdose reversal agent. Emphasize the importance of doing this before an opioid emergency happens, so the patient and caregiver will know what to do.

Hyperalgesia and Allodynia
Inform patients and caregivers not to increase opioid dosage without first consulting a clinician. Advise patients to seek medical attention if they experience symptoms of hyperalgesia, including worsening pain, increased sensitivity to pain, or new pain [see Warnings and Precautions (5.10); Adverse Reactions (6.2)].

Serotonin Syndrome
Inform patients that opioids could cause a rare but potentially life-threatening condition resulting from concomitant administration of serotonergic drugs. Warn patients of the symptoms and signs of serotonin syndrome, and to seek medical attention right away if symptoms develop. Instruct patients to inform their healthcare providers if they are taking, or plan to take serotonergic medications [see Warnings and Precautions (5.11) and Drug Interactions (7)].

MAOI Interaction
Inform patients to avoid taking fentanyl transdermal system while using any drugs that inhibit monoamine oxidase. Patients should not start MAOIs while taking fentanyl transdermal system [see Drug Interactions (7)].

Important Administration Instructions
Advise patients never to change the dose of fentanyl transdermal system or the number of patches applied to the skin unless instructed to do so by the prescribing healthcare professional.

Warnings About Heat
Warn patients of the potential for temperature-dependent increases in fentanyl release from the patch that could result in an overdose of fentanyl. Instruct patients to contact their healthcare provider if they develop a high fever. Instruct patients to:

- avoid strenuous exertion that can increase body temperature while wearing the patch
- avoid exposing the fentanyl transdermal system application site and surrounding area to direct external heat sources including heating pads, electric blankets, sunbathing, heat or tanning lamps, saunas, hot tubs or hot baths, and heated waterbeds.

Important Discontinuation Instructions
In order to avoid developing withdrawal symptoms, instruct patients not to discontinue fentanyl transdermal system without first discussing a tapering plan with the prescriber [see Dosage and Administration (2.9)].

Driving or Operating Heavy Machinery
Inform patients that fentanyl transdermal system may impair the ability to perform potentially hazardous activities such as driving a car or operating heavy machinery. Advise patients not to perform such tasks until they know how they will react to the medication [see Warnings and Precautions (5.22)].

Constipation
Advise patients of the potential for severe constipation, including management instructions and when to seek medical attention [see Adverse Reactions (6), Clinical Pharmacology (12.2)].

Adrenal Insufficiency
Inform patients that opioids could cause adrenal insufficiency, a potentially life-threatening condition. Adrenal insufficiency may present with non-specific symptoms and signs such as nausea, vomiting, anorexia, fatigue, weakness, dizziness, and low blood pressure. Advise patients to seek medical attention if they experience a constellation of these symptoms [see Warnings and Precautions (5.13)].

Hypotension
Inform patients that fentanyl transdermal system may cause orthostatic hypotension and syncope. Instruct patients how to recognize symptoms of low blood pressure and how to reduce the risk of serious consequences should hypotension occur (e.g., sit or lie down, carefully rise from a sitting or lying position) [see Warnings and Precautions (5.14)].

Anaphylaxis
Inform patients that anaphylaxis, including anaphylactic shock, has been reported with ingredients contained in fentanyl transdermal system. Advise patients how to recognize such a reaction and when to seek medical attention [see Contraindications (4), Adverse Reactions (6)].

Pregnancy
Neonatal Opioid Withdrawal Syndrome
Inform female patients of reproductive potential that use of fentanyl transdermal system for an extended period of time during pregnancy can result in neonatal opioid withdrawal syndrome, which may be life-threatening if not recognized and treated [see Warnings and Precautions (5.5), Use in Specific Populations (8.1)].

Embryo-Fetal Toxicity
Inform female patients of reproductive potential that fentanyl transdermal system can cause fetal harm and to inform their healthcare provider of known or suspected pregnancy [see Use in Specific Populations (8.1)].

Lactation
Advise patients that breastfeeding is not recommended during treatment with fentanyl transdermal system [see Use in Specific Populations (8.2)].

Infertility
Inform patients that use of opioids for an extended period of time may cause reduced fertility. It is not known whether these effects on fertility are reversible [see Use in Specific Populations (8.3)].

Revised: 12/2025

An electronic copy of this medication guide can be obtained from www.mallinckrodt.com/Medguide/X30000067.pdf or by calling 1-800-778-7898 for alternate delivery options.

Medication Guide
Fentanyl Transdermal System, CII
(fĕn´ tә-nĭl)

Fentanyl transdermal system is:

- A strong prescription pain medicine that contains an opioid (narcotic) that is used to manage severe and persistent pain that requires an extended treatment period with a daily opioid pain medicine, in people who are already regularly using opioid pain medicine when other pain medicines do not treat your pain well enough or you cannot tolerate them.
- A long-acting (extended-release) opioid pain medicine that can put you at risk for overdose and death. Even if you take your dose correctly as prescribed you are at risk for opioid addiction, abuse, and misuse that can lead to death.
- Not to be used on an “as needed” basis.

Important information about fentanyl transdermal system:

- Get emergency help or call 911 right away if you use too much fentanyl transdermal system (overdose). When you first start taking fentanyl transdermal system, when your dose is changed, or if you take too much (overdose), serious or life-threatening breathing problems that can lead to death may occur. Ask your healthcare provider about medicines like naloxone or nalmefene that can be used in an emergency to reverse an opioid overdose.
- Taking fentanyl transdermal system with other opioid medicines, benzodiazepines, gabapentinoids (gabapentin or pregabalin), alcohol, or other central nervous system depressants (including street drugs) may cause severe drowsiness, decreased awareness, breathing difficulties, with slow or shallow breathing, coma, and death.
- Never give anyone else your fentanyl transdermal system. They could die from taking it. Selling or giving away fentanyl transdermal system is against the law.
- Store fentanyl transdermal system, securely, out of sight and reach of children, and in a location not accessible by others, including visitors to the home.
- If the patch accidentally sticks to a family member while in close contact, take the patch off, wash the area with water, and get emergency help right away because an accidental exposure to fentanyl transdermal system can lead to death or other serious medical problems.
- Dispose of expired, unwanted, or unused fentanyl transdermal system, by folding the patch so that the adhesive side of the patch adheres to itself, and immediately flushing down the toilet (if a drug take-back option is not readily available) [see Instructions for Use]. Visit www.fda.gov/drugdisposal for additional information on disposal of unused medicines.

Do not use fentanyl transdermal system if you have:

- severe asthma, trouble breathing, or other lung problems.
- a bowel blockage or have narrowing of the stomach or intestines.

Before applying fentanyl transdermal system, tell your healthcare provider if you have a history of:

- head injury, seizures
- problems urinating
- abuse of street or prescription drugs, alcohol addiction, opioid overdose, or mental health problems.
- liver, kidney, thyroid problems
- pancreas or gallbladder problems

Tell your healthcare provider if you:

- notice your pain getting worse. If your pain gets worse after you use fentanyl transdermal system, do not use more of fentanyl transdermal system without first talking to your healthcare provider. Talk to your healthcare provider if the pain that you have increases, if you feel more sensitive to pain, or if you have new pain after using fentanyl transdermal system.
- have a fever
- are pregnant or planning to become pregnant. Use of fentanyl transdermal system for an extended period of time during pregnancy can cause withdrawal symptoms in your newborn baby that could be life-threatening if not recognized and treated.
- are breastfeeding. Not recommended during treatment with fentanyl transdermal system. It may harm your baby.
- are living in a household where there are small children or someone who has abused street or prescription drugs.
- are taking prescription or over-the-counter medicines, vitamins, or herbal supplements. Taking fentanyl transdermal system with certain other medicines can cause serious side effects that could lead to death.

When using fentanyl transdermal system:

- Do not change your dose. Apply fentanyl transdermal system exactly as prescribed by your healthcare provider. Use the lowest dose possible for the shortest time needed.
- See the detailed Instructions for Use for information about how to apply and dispose of the fentanyl transdermal system. Visit www.fda.gov/drugdisposal for additional information on disposal of unused medicines.
- Do not apply more than 1 patch at the same time unless your healthcare provider tells you to.
- You should wear the fentanyl transdermal system continuously for 3 days, unless advised otherwise by your healthcare provider.
- Do not cut, break, chew, crush, dissolve, snort, or inject fentanyl transdermal system because this may cause you to overdose and die.
- Call your healthcare provider if the dose you are using does not control your pain.
- Do not stop using fentanyl transdermal system without talking to your healthcare provider.

While using fentanyl transdermal system DO NOT:

- Take hot baths or sunbathe, use hot tubs, saunas, heating pads, electric blankets, heated waterbeds, or tanning lamps, or engage in exercise that increases your body temperature. These can cause an overdose that can lead to death.
- Drive or operate heavy machinery, until you know how fentanyl transdermal system affects you. Fentanyl transdermal system can make you sleepy, dizzy, or lightheaded.
- Drink alcohol or use prescription or over-the-counter medicines that contain alcohol. Using products containing alcohol during treatment with fentanyl transdermal system may cause you to overdose and die.

The possible side effects of fentanyl transdermal system are:

- constipation, nausea, sleepiness, vomiting, tiredness, headache, dizziness, abdominal pain, itching, redness, or rash where the patch is applied. Call your healthcare provider if you have any of these symptoms and they are severe.

Get emergency medical help or call 911 right away if you have:

- trouble breathing, shortness of breath, fast heartbeat, chest pain, swelling of your face, tongue or throat, extreme drowsiness, light-headedness when changing positions, feeling faint, agitation, high body temperature, trouble walking, stiff muscles, or mental changes such as confusion.

These are not all the possible side effects of fentanyl transdermal system. Call your healthcare provider for medical advice about side effects. You may report side effects to FDA at
1-800-FDA-1088. For more information go to dailymed.nlm.nih.gov

Manufactured by: LTS Lohmann Therapy Systems, Corp., W. Caldwell, NJ 07006

Manufactured for: SpecGx LLC, Webster Groves, MO 63119 USA, www.mallinckrodt.com or call 1-800-778-7898

X30000067

Mallinckrodt™
Pharmaceuticals

This Medication Guide has been approved by the U.S. Food and Drug Administration.
Revised: 10/2025

Instructions for Use
Fentanyl Transdermal System CII

Be sure that you read, understand, and follow these Instructions for Use before you apply fentanyl transdermal system. Talk to your healthcare provider or pharmacist if you have any questions.

Important information about the fentanyl transdermal system appearance:

- Fentanyl transdermal systems are a rectangular, opaque patch with rounded corners.
- Fentanyl transdermal system comes in 7 different dosage strengths and sizes:
  - 12 mcg/hr: Fentanyl Transdermal System 12 mcg/hr printed in green
  - 25 mcg/hr: Fentanyl Transdermal System 25 mcg/hr printed in green
  - 37.5 mcg/hr: Fentanyl Transdermal System 37.5 mcg/hr printed in green
  - 50 mcg/hr: Fentanyl Transdermal System 50 mcg/hr printed in green
  - 62.5 mcg/hr: Fentanyl Transdermal System 62.5 mcg/hr printed in green
  - 75 mcg/hr: Fentanyl Transdermal System 75 mcg/hr printed in green
  - 100 mcg/hr: Fentanyl Transdermal System 100 mcg/hr printed in green
- The 12 mcg/hour system has a green border.
- The 25, 37.5, 50, 62.5, 75 and 100 mcg/hour systems have green stripes that increase in number with each sequential increasing dosage strength.

Parts of the fentanyl transdermal system:

Before applying fentanyl transdermal system

- Each fentanyl transdermal system is sealed in its own protective pouch. Do not remove a fentanyl transdermal system from the pouch until you are ready to use it.
- Do not use a fentanyl transdermal system if the pouch seal is broken or the patch is cut, damaged or changed in any way.
- Fentanyl transdermal systems are available in 7 different dosage strengths and patch sizes. Make sure you have the right dose patch or patches that have been prescribed for you.

Applying a fentanyl transdermal system

1. Skin areas where the fentanyl transdermal system may be applied:

For adults:

- Put the patch on the chest, back, flank (sides of the waist), or upper arm in a place where there is no hair (see Figures 1-4).

For children (and adults with mental impairment):

- Put the patch on the upper back (see Figure 2). This will lower the chances that the child will remove the patch and put it in their mouth.

For adults and children:

- Do not put a fentanyl transdermal system on skin that is very oily, burned, broken out, cut, irritated, or damaged in any way.
- Avoid sensitive areas or those that move around a lot. If there is hair, do not shave (shaving irritates the skin). Instead, clip hair as close to the skin as possible (see Figure 5).
- Talk to your healthcare provider if you have questions about skin application sites.

2. Prepare to apply a fentanyl transdermal system:

- Choose the time of day that is best for you to apply fentanyl transdermal system. Change it at about the same time of day (3 days or 72 hours after you apply the patch) or as directed by your healthcare provider.
- Do not wear more than one fentanyl transdermal system at a time unless your healthcare provider tells you to do so. Before applying a new fentanyl transdermal system, remove the patch you have been wearing.
- Clean the skin area with clear water only. Pat skin completely dry. Do not use anything on the skin such as soaps, lotions, oils, or alcohol before the patch is applied.

3. Open the pouch: Fold and tear at slit, or cut at line taking care not to cut the patch. Remove the fentanyl transdermal system. Each fentanyl transdermal system is sealed in its own protective pouch. Do not remove the fentanyl transdermal system from the pouch until you are ready to use it (see Figure 6).

4. Peel: Peel off both parts of the protective liner from the patch. Each fentanyl transdermal system has a clear plastic backing that can be peeled off in two pieces. This covers the sticky side of the patch. Carefully peel this backing off. Throw the clear plastic backing away. Touch the sticky side of the fentanyl transdermal system as little as possible (see Figure 7).

5. Press: Press the patch onto the chosen skin site with the palm of your hand and hold there for at least 30 seconds (see Figure 8). Make sure it sticks well, especially at the edges.

- Fentanyl transdermal system may not stick to all people. You need to check the patch often to make sure that it is sticking well to the skin.
- If the patch falls off right away after applying, throw it away and put a new one on at a different skin site. See the section below called "Disposing of a fentanyl transdermal system".
- If you have a problem with the patch not sticking
  - Apply first aid tape only to the edges of the patch.
  - If you continue to have problems with the patch not sticking, you may cover the patch with a transparent adhesive film dressing such as Bioclusive™ or Tegaderm™. These are special see-through adhesive dressings. Never cover a fentanyl transdermal system with any other bandage or tape. Remove the backing from the Bioclusive™ or Tegaderm™ dressing and place it carefully over the fentanyl transdermal system, smoothing it over the patch and your skin.
- If your patch falls off before 3 days (72 hours) of use, dispose of (throw away) properly. See the section below "Disposing of a fentanyl transdermal system". Apply a new fentanyl transdermal system on at a different skin site. Be sure to let your healthcare provider know that this has happened, and do not replace the new patch until 3 days (72 hours) after you put it on (or as directed by your healthcare provider).

6. Wash your hands when you have finished applying a fentanyl transdermal system.

7. Remove a fentanyl transdermal system after wearing it for 3 days (72 hours). Dispose of the used patch right away. See the section below "Disposing of a fentanyl transdermal system". Choose a different skin site to apply a new fentanyl transdermal system. Repeat Steps 2 through 6 above when applying a new fentanyl transdermal system.

Do not apply the new patch to the same place as the last one.

Water and fentanyl transdermal system

- You can bathe, swim or shower while you are wearing a fentanyl transdermal system. If the patch falls off before 3 days (72 hours) after application, dispose of properly. See the section below “Disposing of a fentanyl transdermal system”. Apply a new fentanyl transdermal system on at a different skin site. Be sure to let your healthcare provider know that this has happened, and do not replace the new patch until 3 days (72 hours) after you put it on (or as directed by your healthcare provider).

Disposing of a fentanyl transdermal system

- Fold the used fentanyl transdermal system in half so that the sticky side sticks to itself (see Figure 9). Flush the used fentanyl transdermal system down the toilet right away (see Figure 10). A used fentanyl transdermal system can be very dangerous for or lead to death in babies, children, pets, and adults who have not been prescribed fentanyl transdermal system.
- Throw away any fentanyl transdermal systems that are left over from your prescription as soon as they are no longer needed. Remove the leftover patches from their protective pouch and remove the protective liner. Fold the patches in half with the sticky sides together, and flush the patches down the toilet. Do not flush the pouch or the protective liner down the toilet. These items can be thrown away in a trash can.

This Instructions for Use has been approved by the U.S. Food and Drug Administration.

Mallinckrodt, the “M” brand mark and the Mallinckrodt Pharmaceuticals logo are trademarks of a Mallinckrodt company.

© 2025 Mallinckrodt.

Bioclusive™ and Tegaderm™ are trademarks of their respective owners.

Rx only

Manufactured by:
LTS Lohmann Therapy Systems, Corp.
W. Caldwell, NJ 07006

Manufactured for:
SpecGx LLC
Webster Groves, MO 63119 USA

Printed in USA

6520730

Issued: 10/2025

Mallinckrodt™
Pharmaceuticals

PRINCIPAL DISPLAY PANEL - 12 mcg/hr

NDC 0406-9112-76
Five (12 mcg/hr) Systems
FENTANYL TRANSDERMAL SYSTEM
12 mcg/hr
Rx only
CII

In vivo delivery of 12 mcg/hr fentanyl for 72 hours

Because serious or life-threatening breathing problems could result,
DO NOT USE FENTANYL TRANSDERMAL SYSTEM:

- For pain that can be treated with immediate-release opioids or non-opioid analgesics
- For intermittant (on an as-needed basis) pain
- For any postoperative pain
- Unless you are opioid tolerant (have been using other narcotic opioid medicines)

Each transdermal system contains: 1.375 mg fentanyl
DO NOT USE IF SEAL ON POUCH IS BROKEN
KEEP OUT OF REACH OF CHILDREN
Read enclosed fentanyl transdermal system Medication Guide for important safety information.

PHARMACIST: Dispense the Medication Guide provided separately to each patient.

For Opioid-Tolerant Patients Only

Mallinckrodt™

0004316

Rev 03/2020

PRINCIPAL DISPLAY PANEL - 25 mcg/hr

NDC 0406-9125-76
Five (25 mcg/hr) Systems
FENTANYL TRANSDERMAL SYSTEM
25 mcg/hr
Rx only
CII

In vivo delivery of 25 mcg/hr fentanyl for 72 hours

Because serious or life-threatening breathing problems could result,
DO NOT USE FENTANYL TRANSDERMAL SYSTEM:

- For pain that can be treated with immediate-release opioids or non-opioid analgesics
- For intermittant (on an as-needed basis) pain
- For any postoperative pain
- Unless you are opioid tolerant (have been using other narcotic opioid medicines)

Each transdermal system contains: 2.75mg fentanyl
DO NOT USE IF SEAL ON POUCH IS BROKEN
KEEP OUT OF REACH OF CHILDREN
Read enclosed fentanyl transdermal system Medication Guide for important safety information.

PHARMACIST: Dispense the Medication Guide provided separately to each patient.

For Opioid-Tolerant Patients Only

Mallinckrodt™

0004317

Rev 03/2020

PRINCIPAL DISPLAY PANEL - 37.5 mcg/hr

NDC 0406-9037-76
Five (37.5 mcg/hr) Systems

FENTANYL TRANSDERMAL SYSTEM

Rx only
37.5 mcg/hr
CII

In vivo delivery of 37.5 mcg/hr fentanyl for 72 hours

Because serious or life-threatening breathing problems could result,
DO NOT USE FENTANYL TRANSDERMAL SYSTEM:

- For pain that can be treated with immediate-release opioids or non-opioid analgesics
- For intermittant (on an as-needed basis) pain
- For any postoperative pain
- Unless you are opioid tolerant (have been using other narcotic opioid medicines)

Each transdermal system contains: 4.125 mg fentanyl
DO NOT USE IF SEAL ON POUCH IS BROKEN
KEEP OUT OF REACH OF CHILDREN
Read enclosed fentanyl transdermal system Medication Guide for important safety information.

PHARMACIST: Dispense the Medication Guide provided separately to each patient.

For Opioid-Tolerant Patients Only

Mallinckrodt™

0004257

Rev 03/2019

PRINCIPAL DISPLAY PANEL - 50 mcg/hr

NDC 0406-9150-76
Five (50 mcg/hr) Systems
FENTANYL TRANSDERMAL SYSTEM
50 mcg/hr
Rx only
CII

In vivo delivery of 50 mcg/hr fentanyl for 72 hours

Because serious or life-threatening breathing problems could result,
DO NOT USE FENTANYL TRANSDERMAL SYSTEM:

- For pain that can be treated with immediate-release opioids or non-opioid analgesics
- For intermittant (on an as-needed basis) pain
- For any postoperative pain
- Unless you are opioid tolerant (have been using other narcotic opioid medicines)

Each transdermal system contains: 5.50mg fentanyl

DO NOT USE IF SEAL ON POUCH IS BROKEN
KEEP OUT OF REACH OF CHILDREN
Read enclosed fentanyl transdermal system Medication Guide for important safety information.

PHARMACIST: Dispense the Medication Guide provided separately to each patient.

For Opioid-Tolerant Patients Only

Mallinckrodt™

0004318

Rev 03/2020

PRINCIPAL DISPLAY PANEL - 62.5 mcg/hr

NDC 0406-9062-76
Five (62.5 mcg/hr) Systems

FENTANYL TRANSDERMAL SYSTEM

Rx only
62.5 mcg/hr
CII

In vivo delivery of 62.5 mcg/hr fentanyl for 72 hours

Because serious or life-threatening breathing problems could
result, DO NOT USE FENTANYL TRANSDERMAL SYSTEM:

- For pain that can be treated with immediate-release opioids or non-opioid analgesics
- For intermittant (on an as-needed basis) pain
- For any postoperative pain
- Unless you are opioid tolerant (have been using other narcotic opioid medicines)

Each transdermal system contains: 6.875 mg fentanyl
DO NOT USE IF SEAL ON POUCH IS BROKEN
KEEP OUT OF REACH OF CHILDREN
Read fentanyl transdermal system Medication Guide for important safety information.

PHARMACIST: Dispense the Medication Guide provided separately to each patient.

For Opioid-Tolerant Patients Only

Mallinckrodt™

0004259

Rev 03/2019

PRINCIPAL DISPLAY PANEL - 75 mcg/hr

NDC 0406-9175-76
Five (75 mcg/hr) Systems
FENTANYL TRANSDERMAL SYSTEM
75 mcg/hr
Rx only
CII

In vivo delivery of 75 mcg/hr fentanyl for 72 hours

Because serious or life-threatening breathing problems could result,
DO NOT USE FENTANYL TRANSDERMAL SYSTEM:

- For pain that can be treated with immediate-release opioids or non-opioid analgesics
- For intermittant (on an as-needed basis) pain
- For any postoperative pain
- Unless you are opioid tolerant (have been using other narcotic opioid medicines)

Each transdermal system contains: 8.25mg fentanyl
DO NOT USE IF SEAL ON POUCH IS BROKEN
KEEP OUT OF REACH OF CHILDREN
Read enclosed fentanyl transdermal system Medication Guide for important safety information.

PHARMACIST: Dispense the Medication Guide provided separately to each patient.

For Opioid-Tolerant Patients Only

Mallinckrodt™

0004319

Rev 03/2020

PRINCIPAL DISPLAY PANEL - 100 mcg/hr

NDC 0406-9100-76
Five (100 mcg/hr) Systems
FENTANYL TRANSDERMAL SYSTEM
100 mcg/hr
Rx only
CII

In vivo delivery of 100 mcg/hr fentanyl for 72 hours

Because serious or life-threatening breathing problems could result,
DO NOT USE FENTANYL TRANSDERMAL SYSTEM:

- For pain that can be treated with immediate-release opioids or non-opioid analgesics
- For intermittant (on an as-needed basis) pain
- For any postoperative pain
- Unless you are opioid tolerant (have been using other narcotic opioid medicines)

Each transdermal system contains: 11.0 mg fentanyl
DO NOT USE IF SEAL ON POUCH IS BROKEN
KEEP OUT OF REACH OF CHILDREN
Read enclosed fentanyl transdermal system Medication Guide for important safety information.

PHARMACIST: Dispense the Medication Guide provided separately to each patient.

For Opioid-Tolerant Patients Only

Mallinckrodt™

0004320

Rev 03/2020